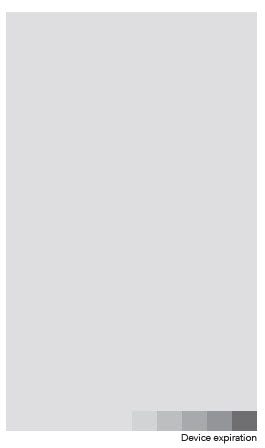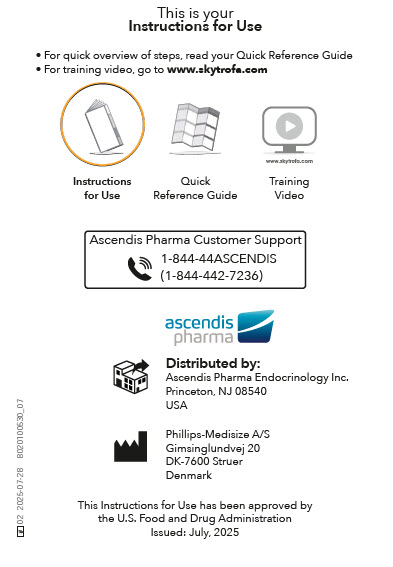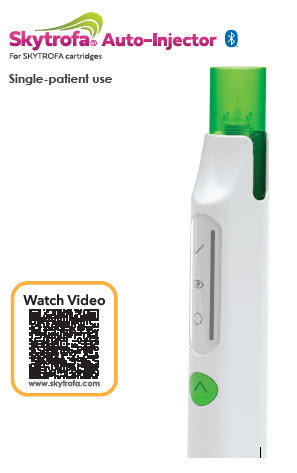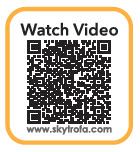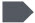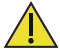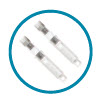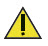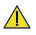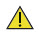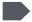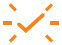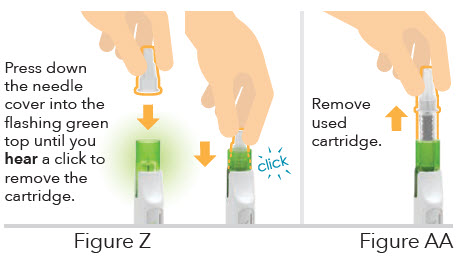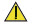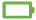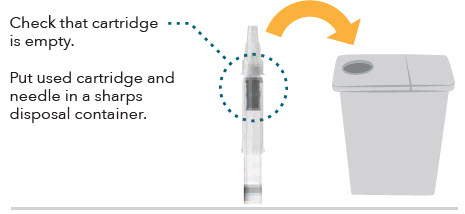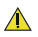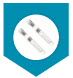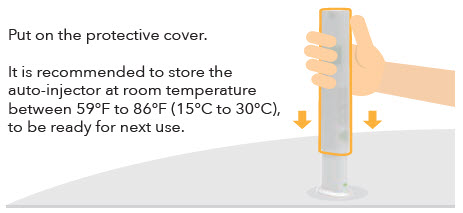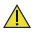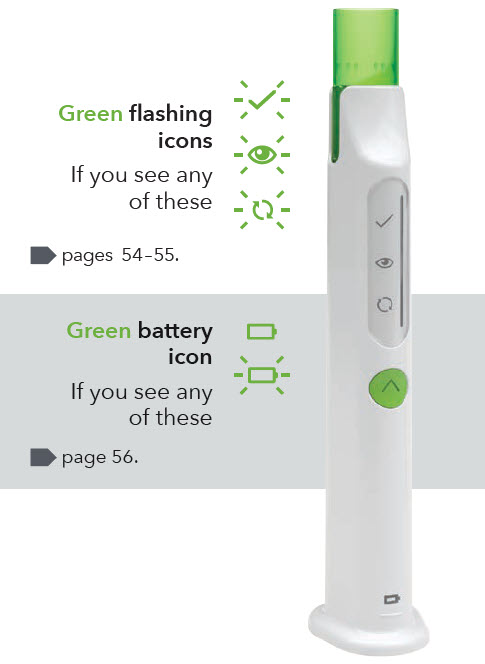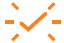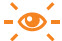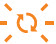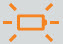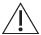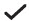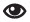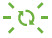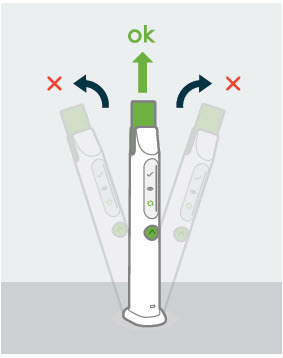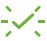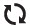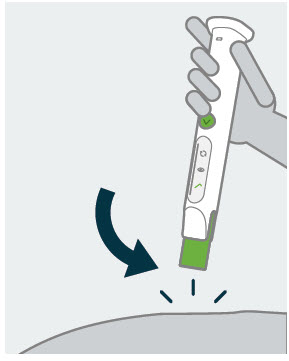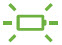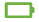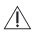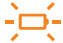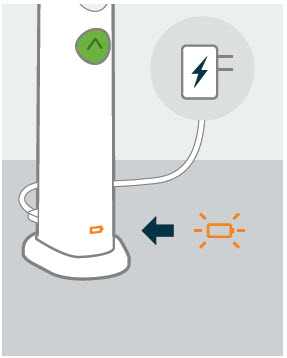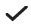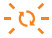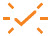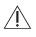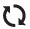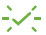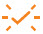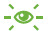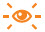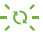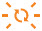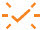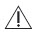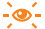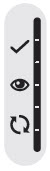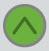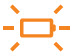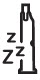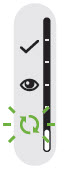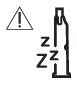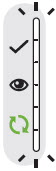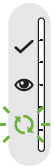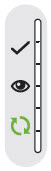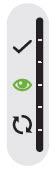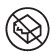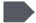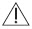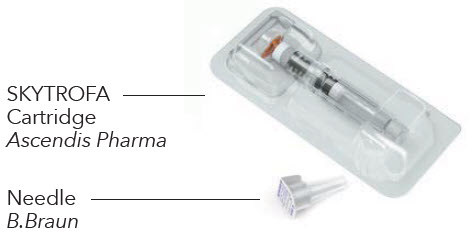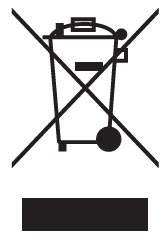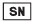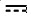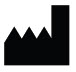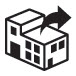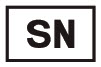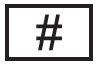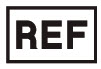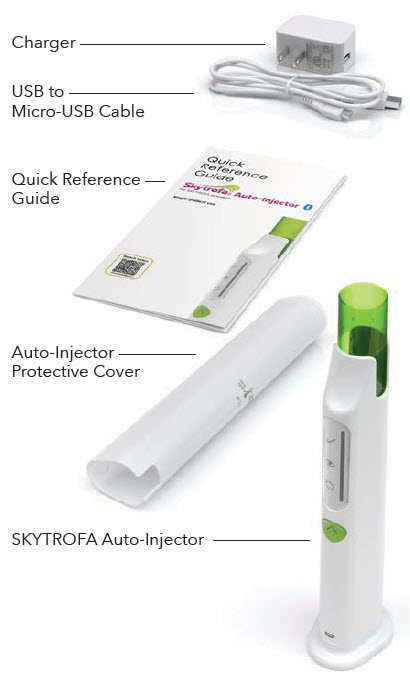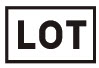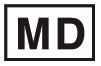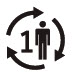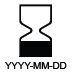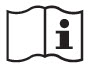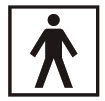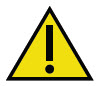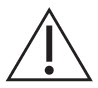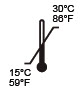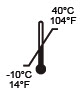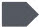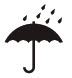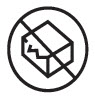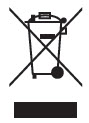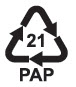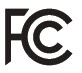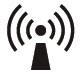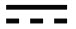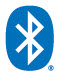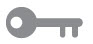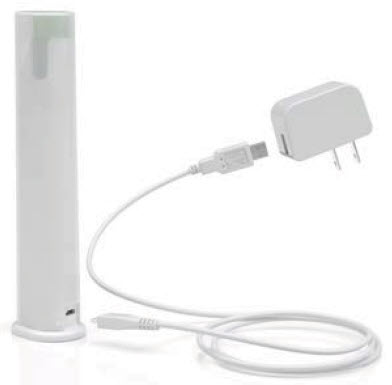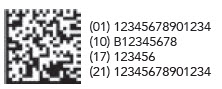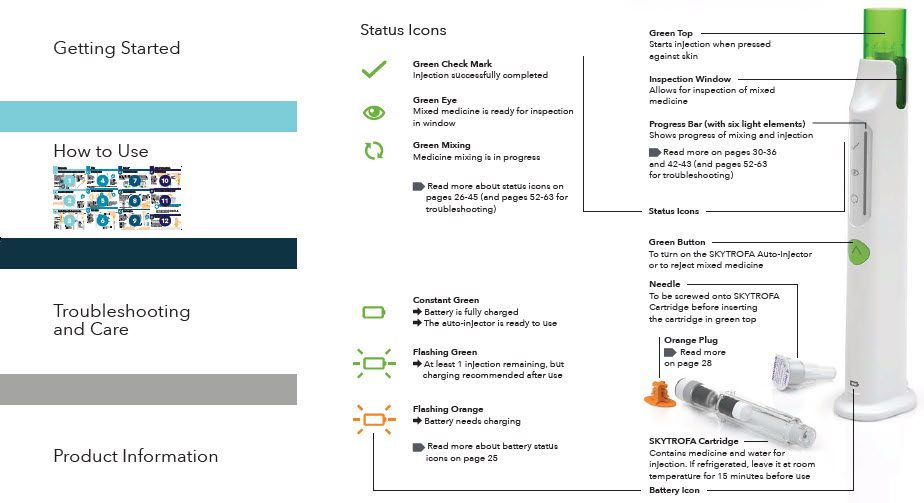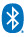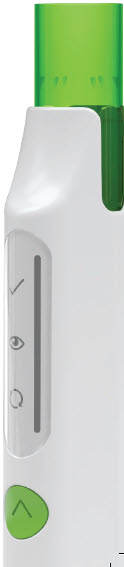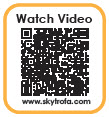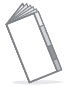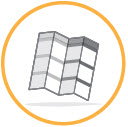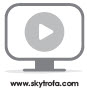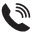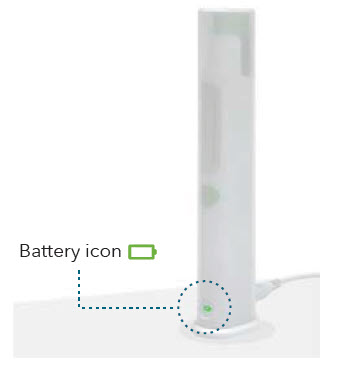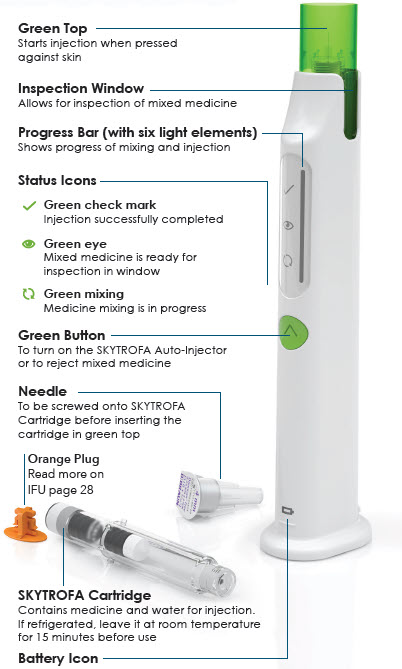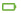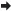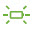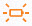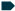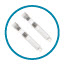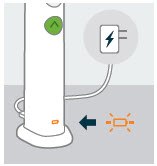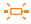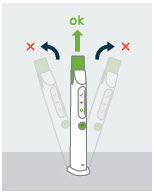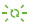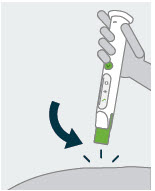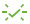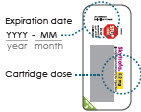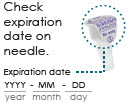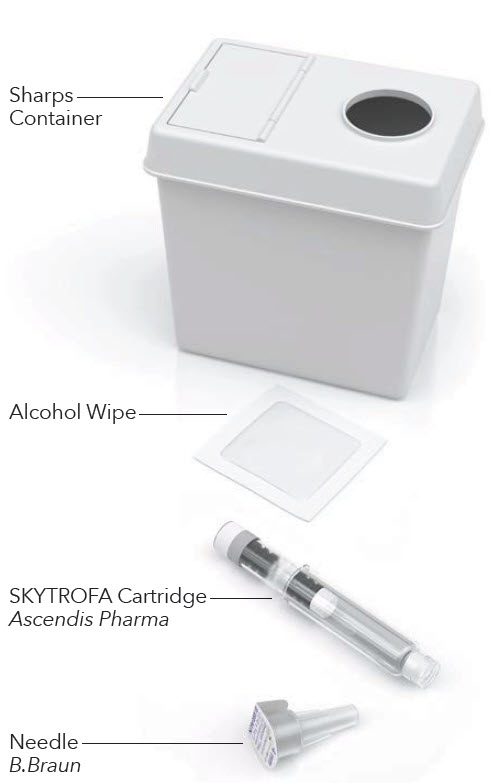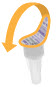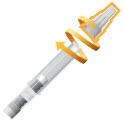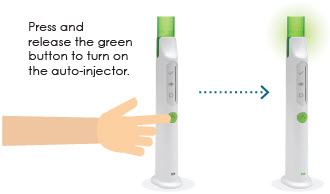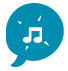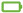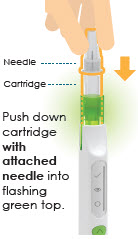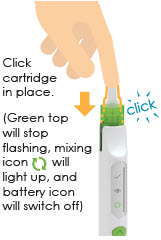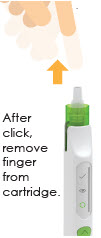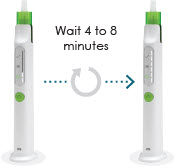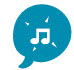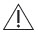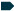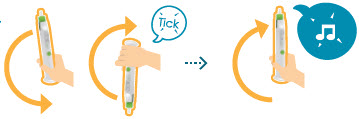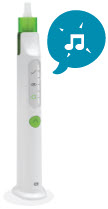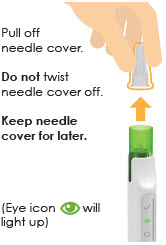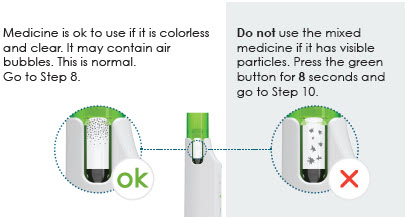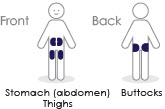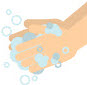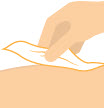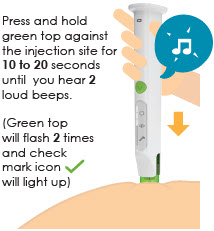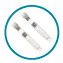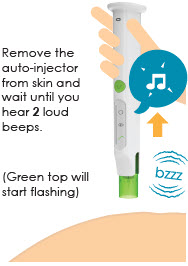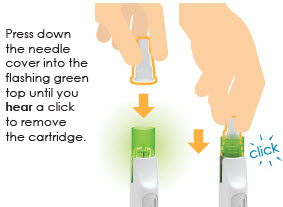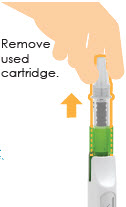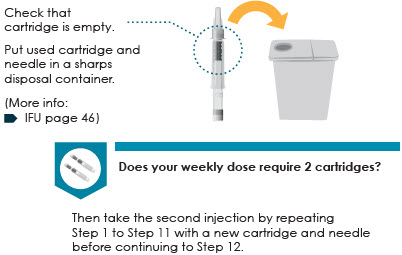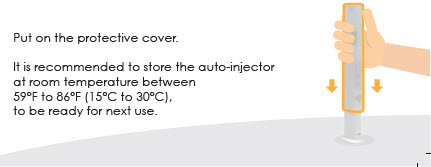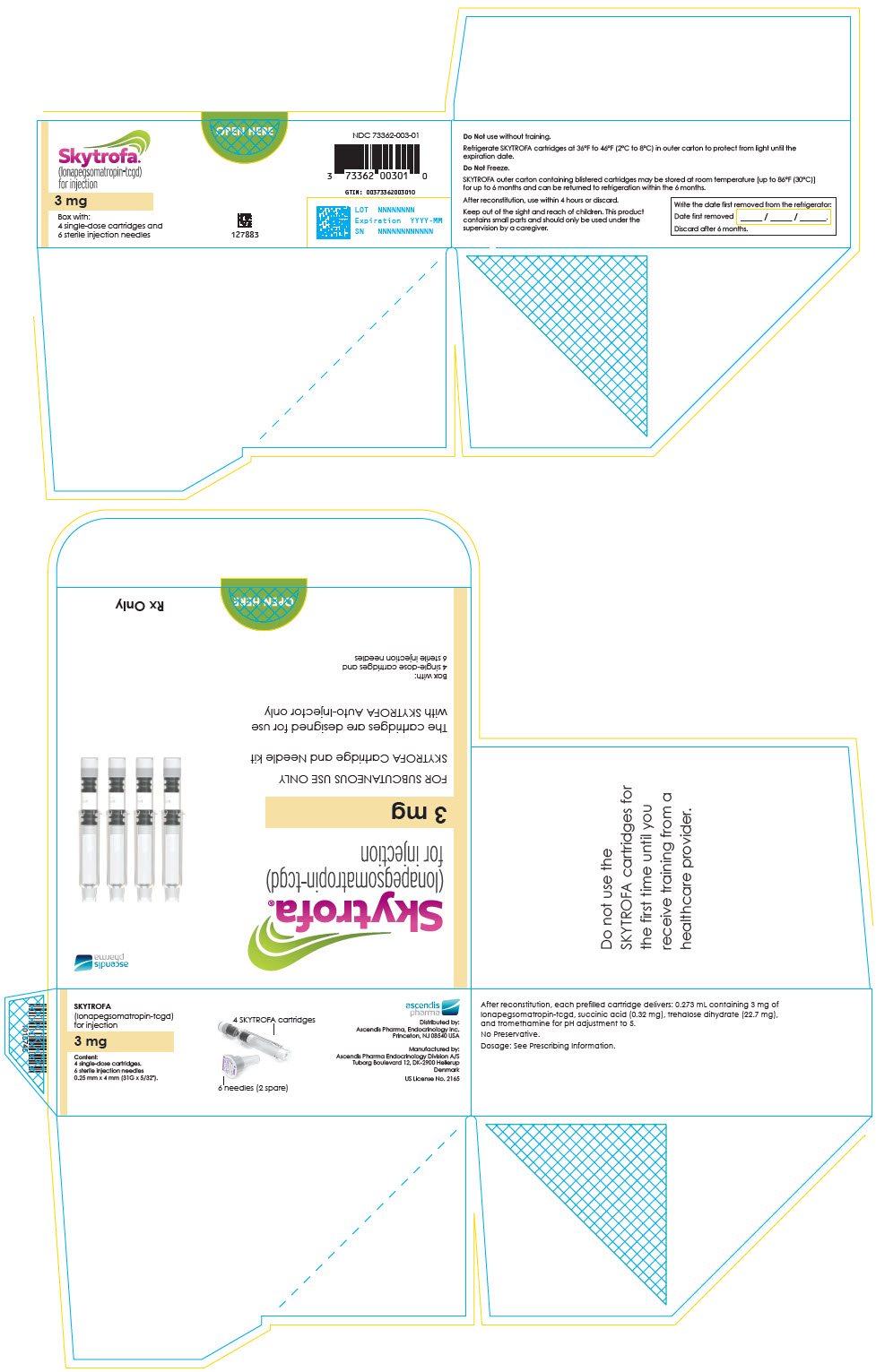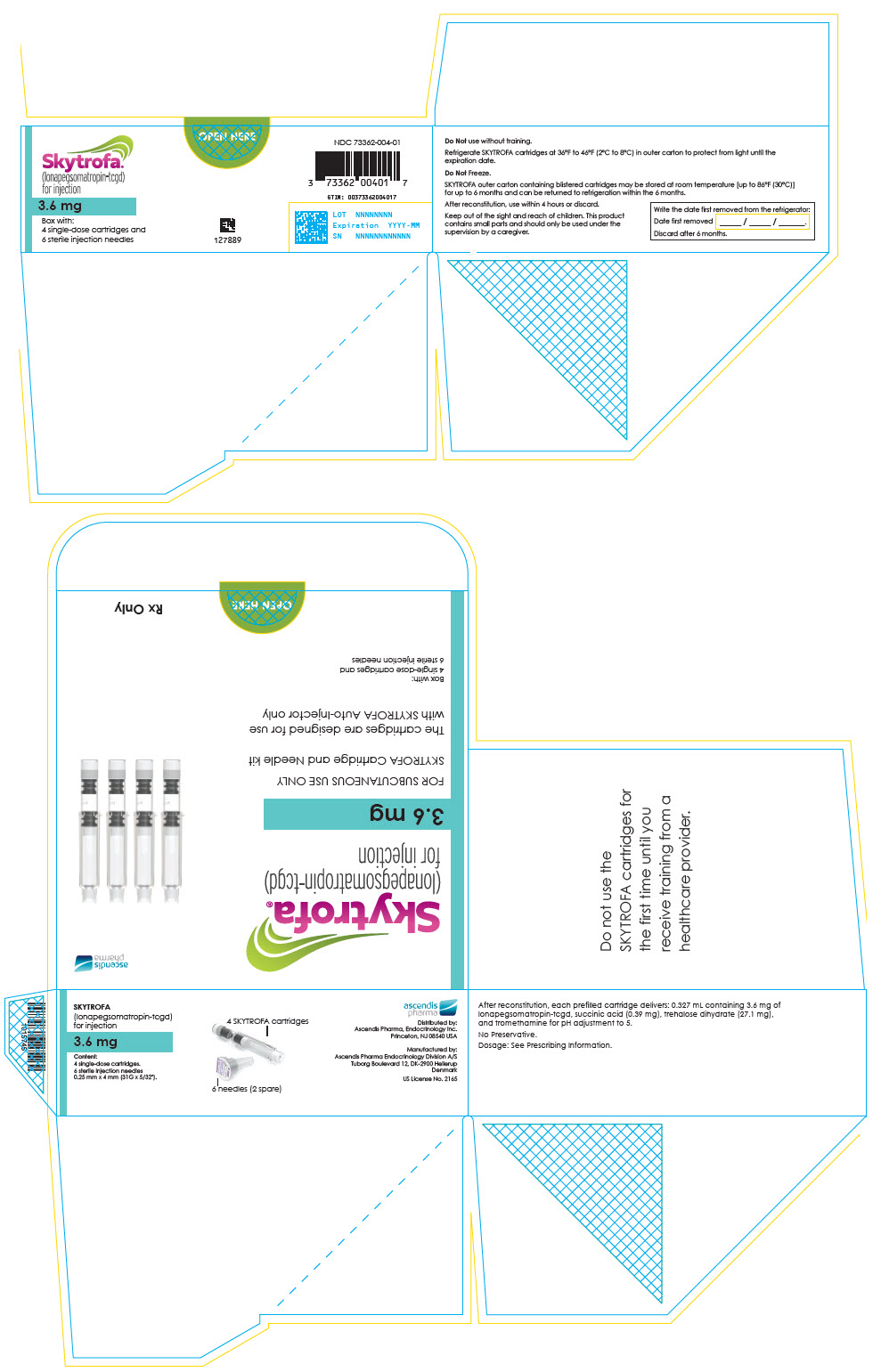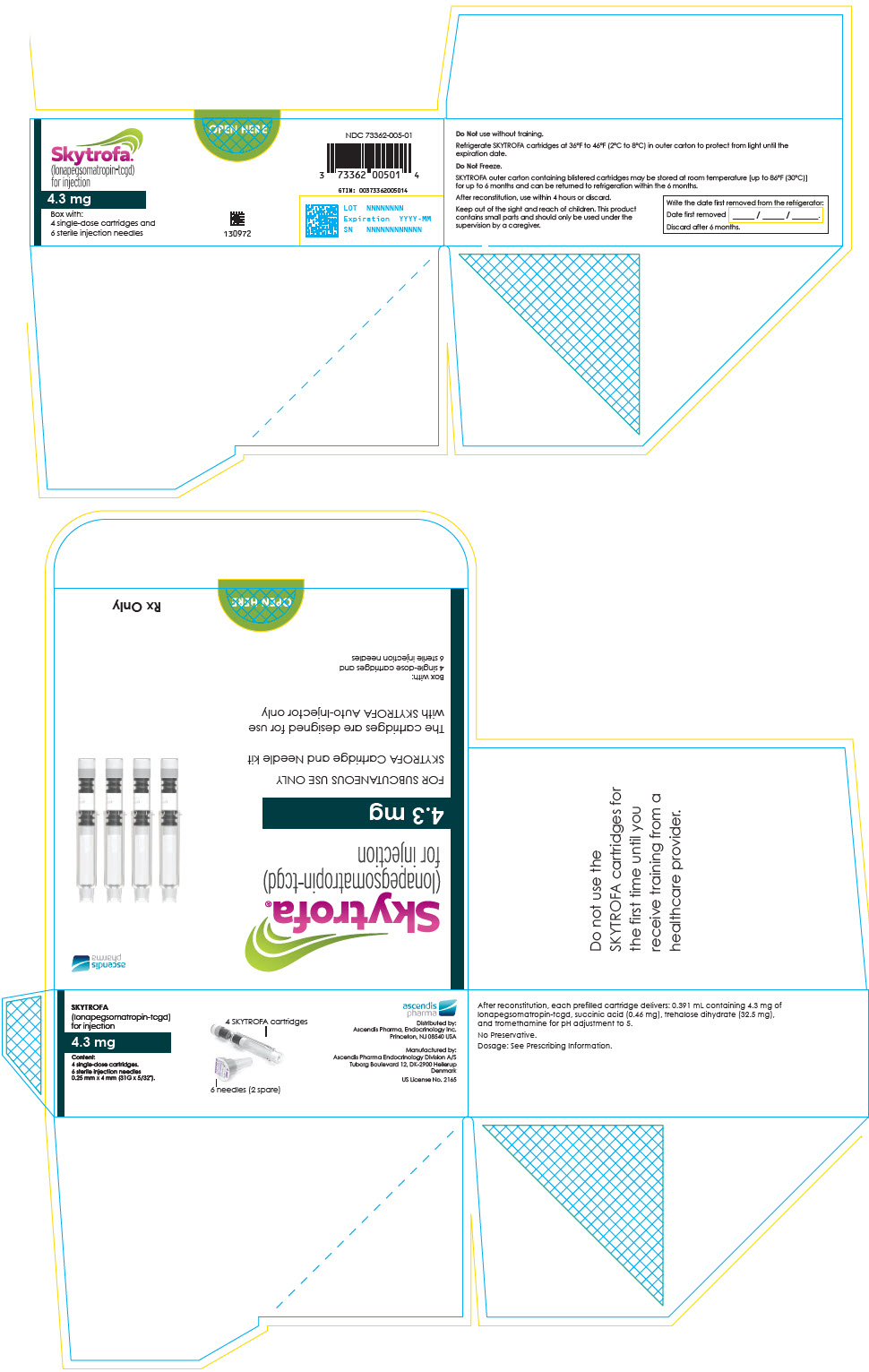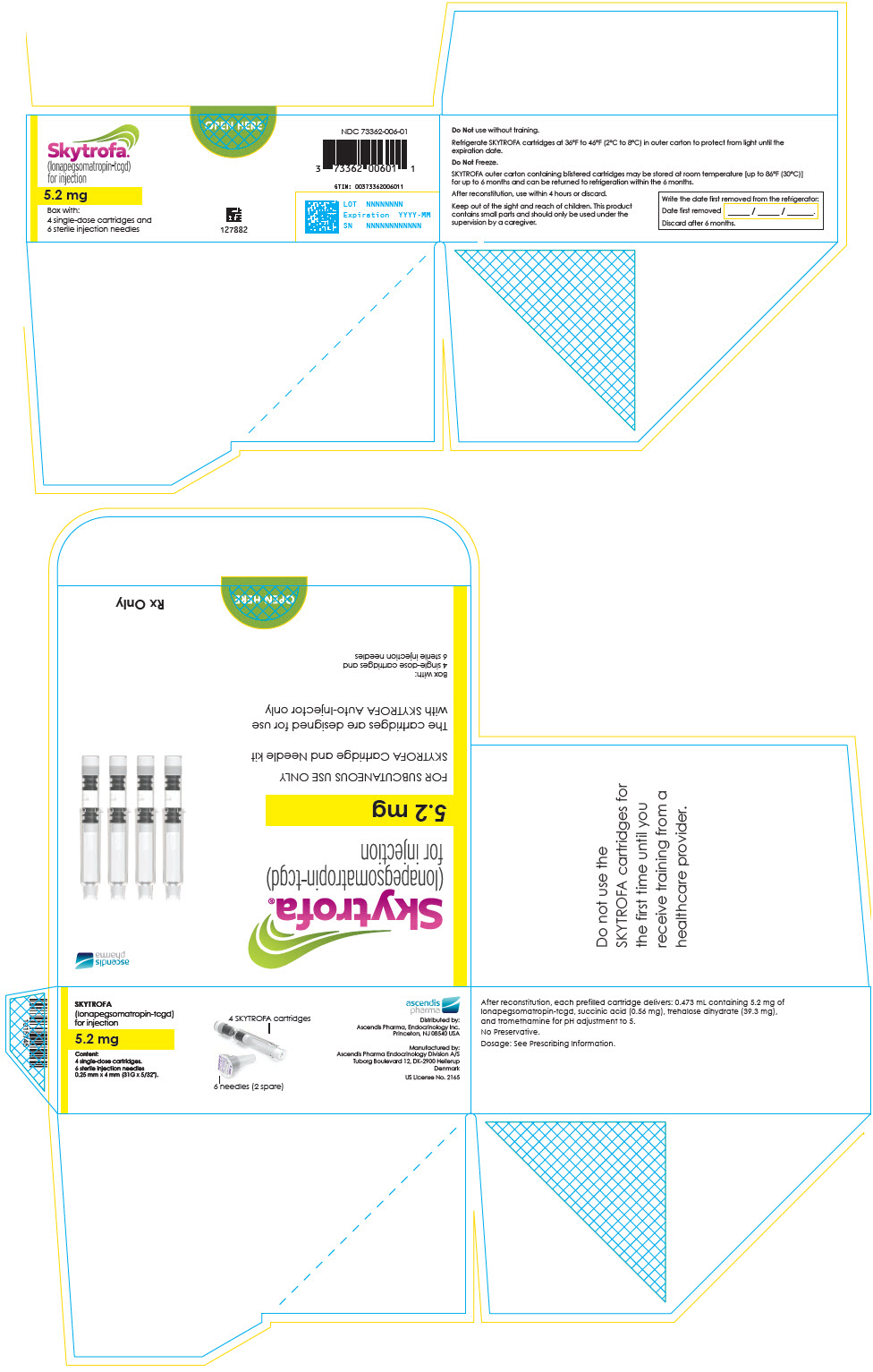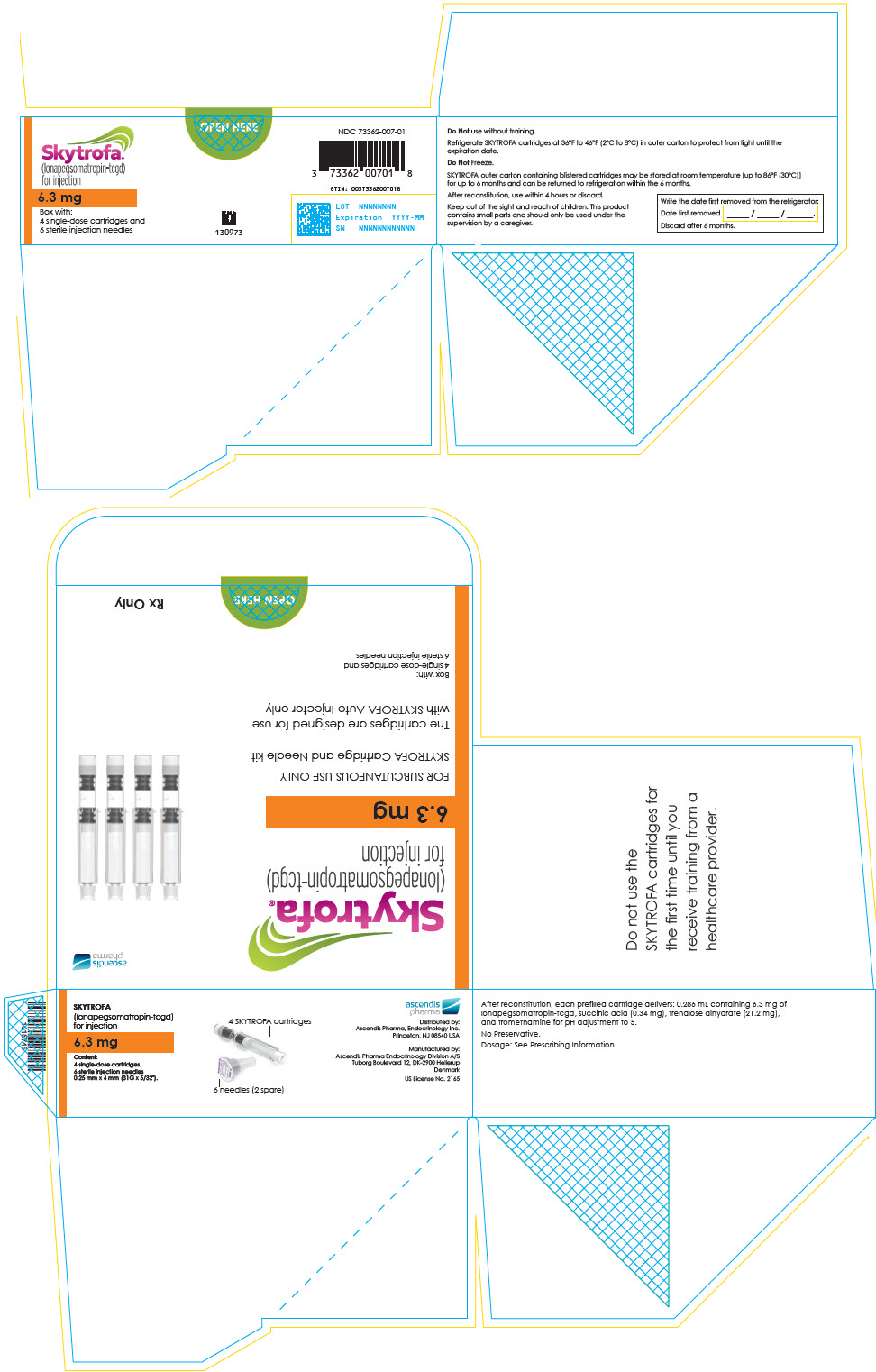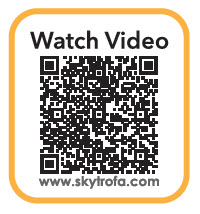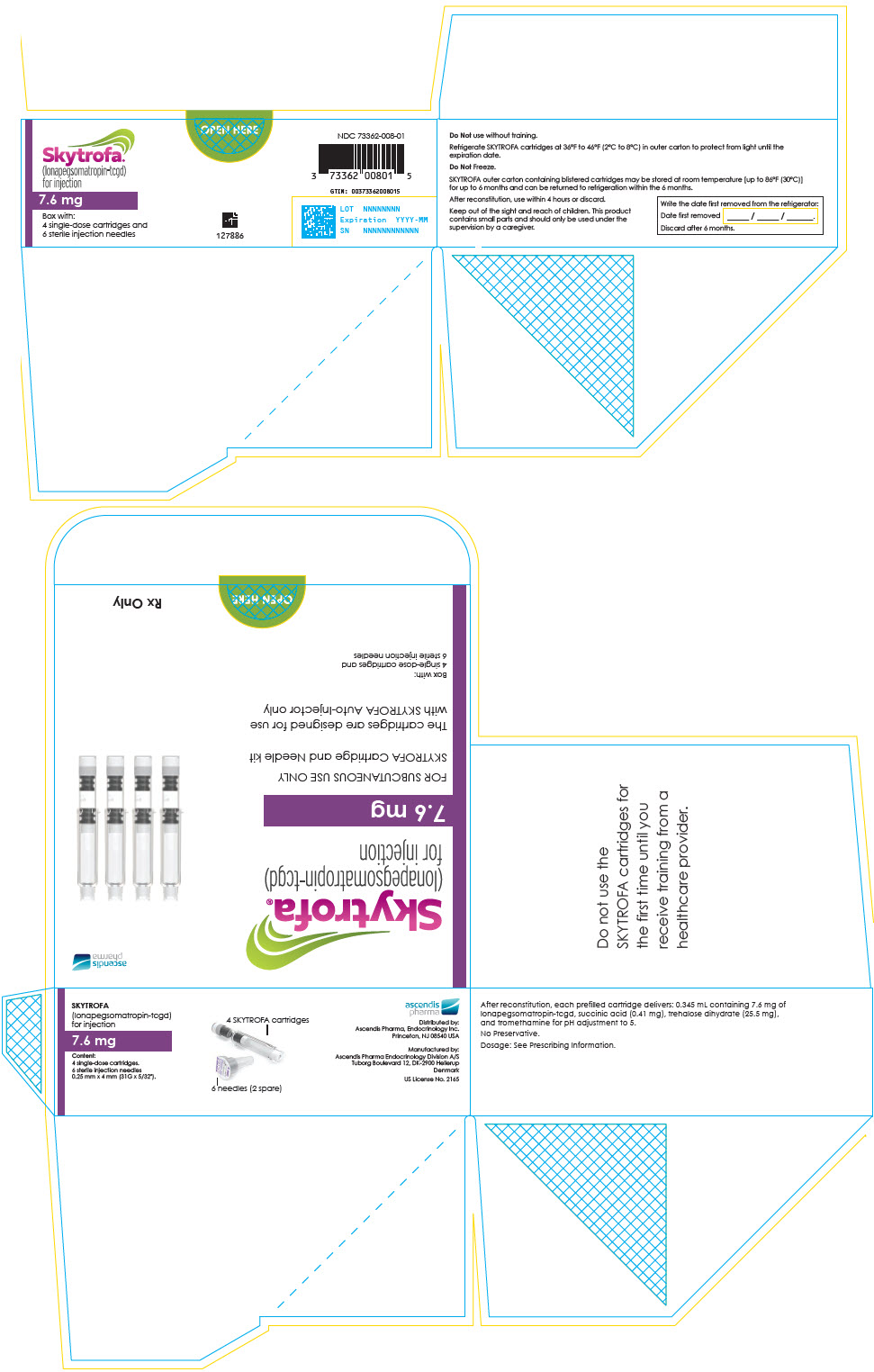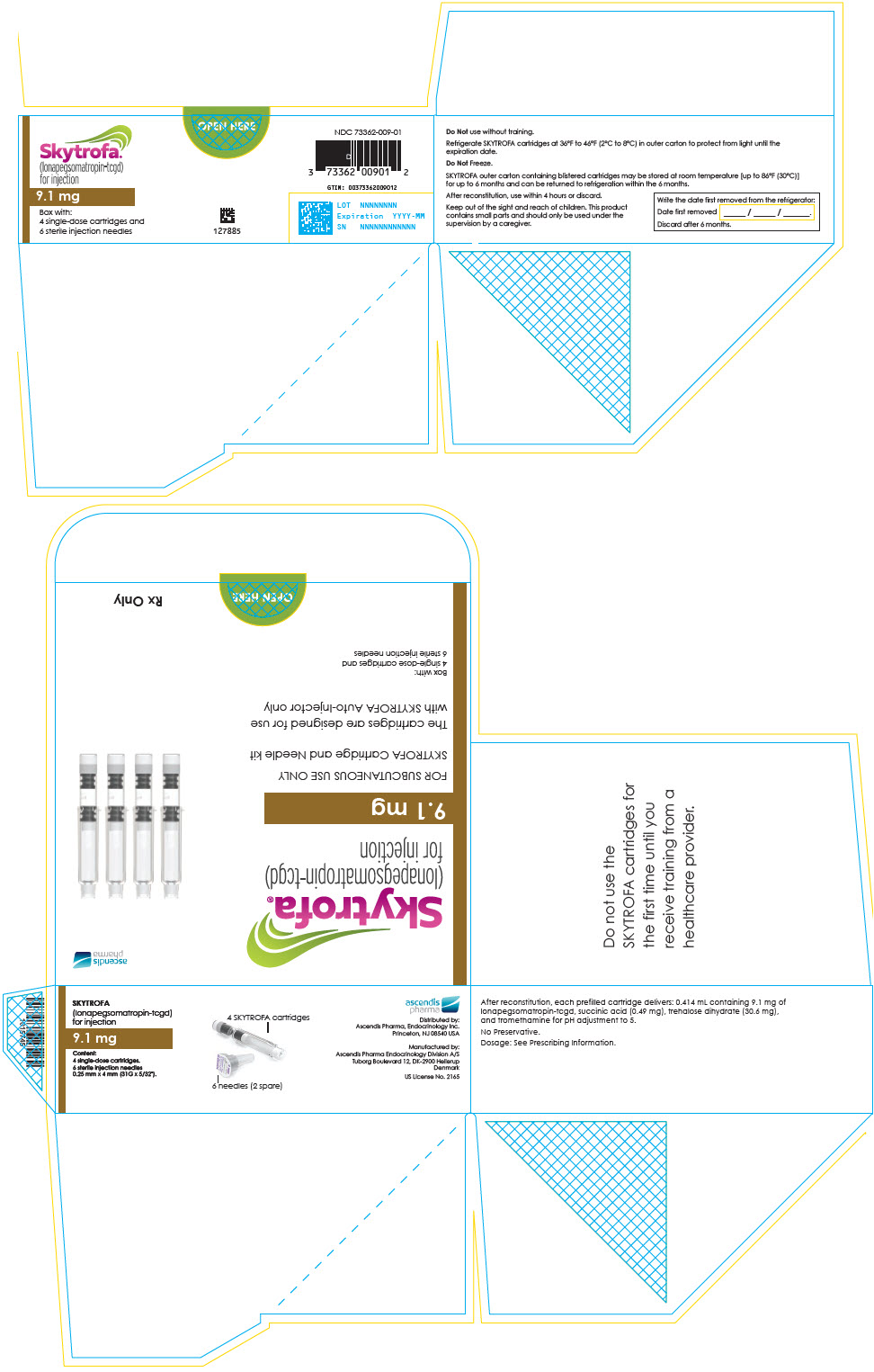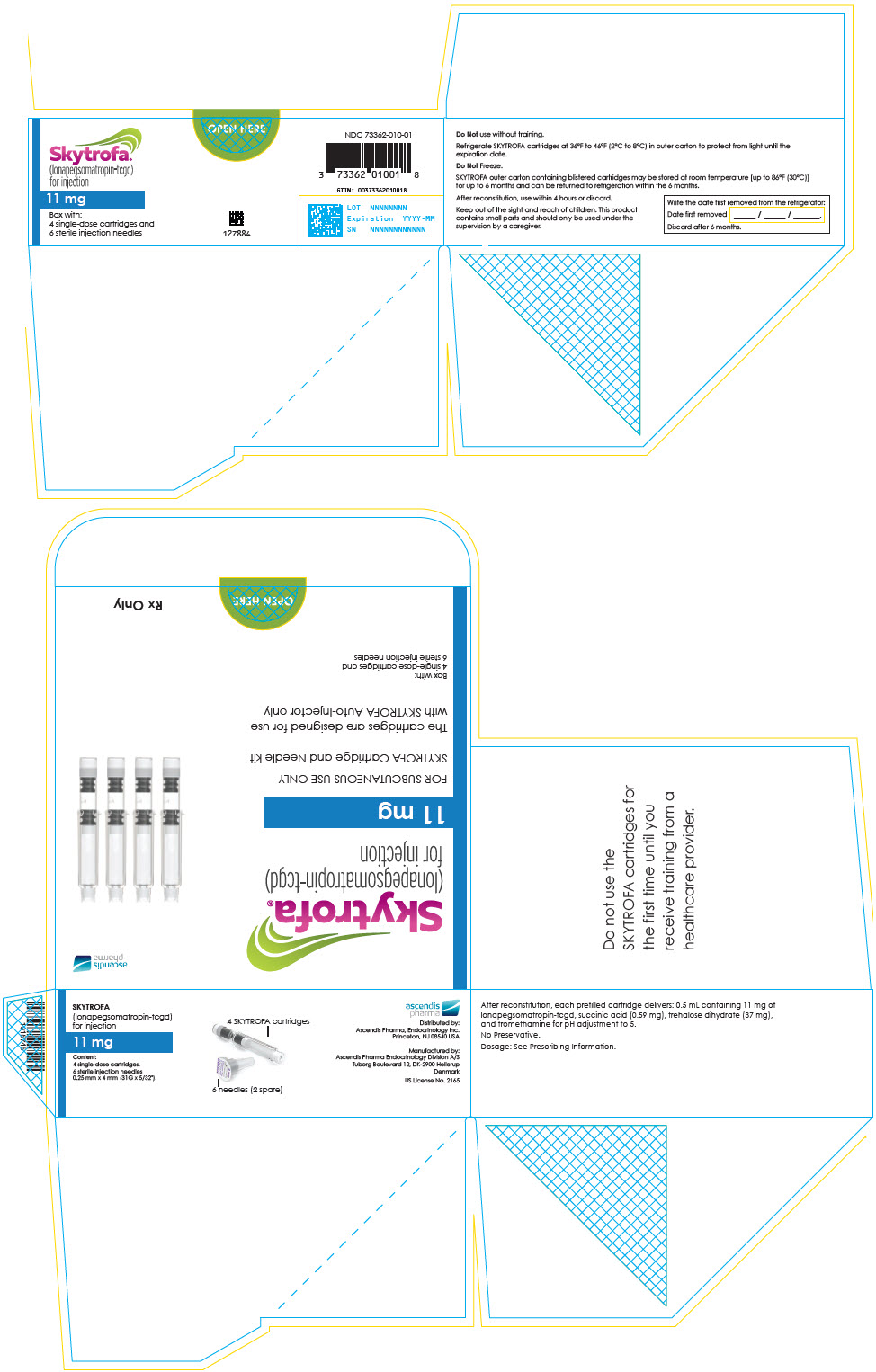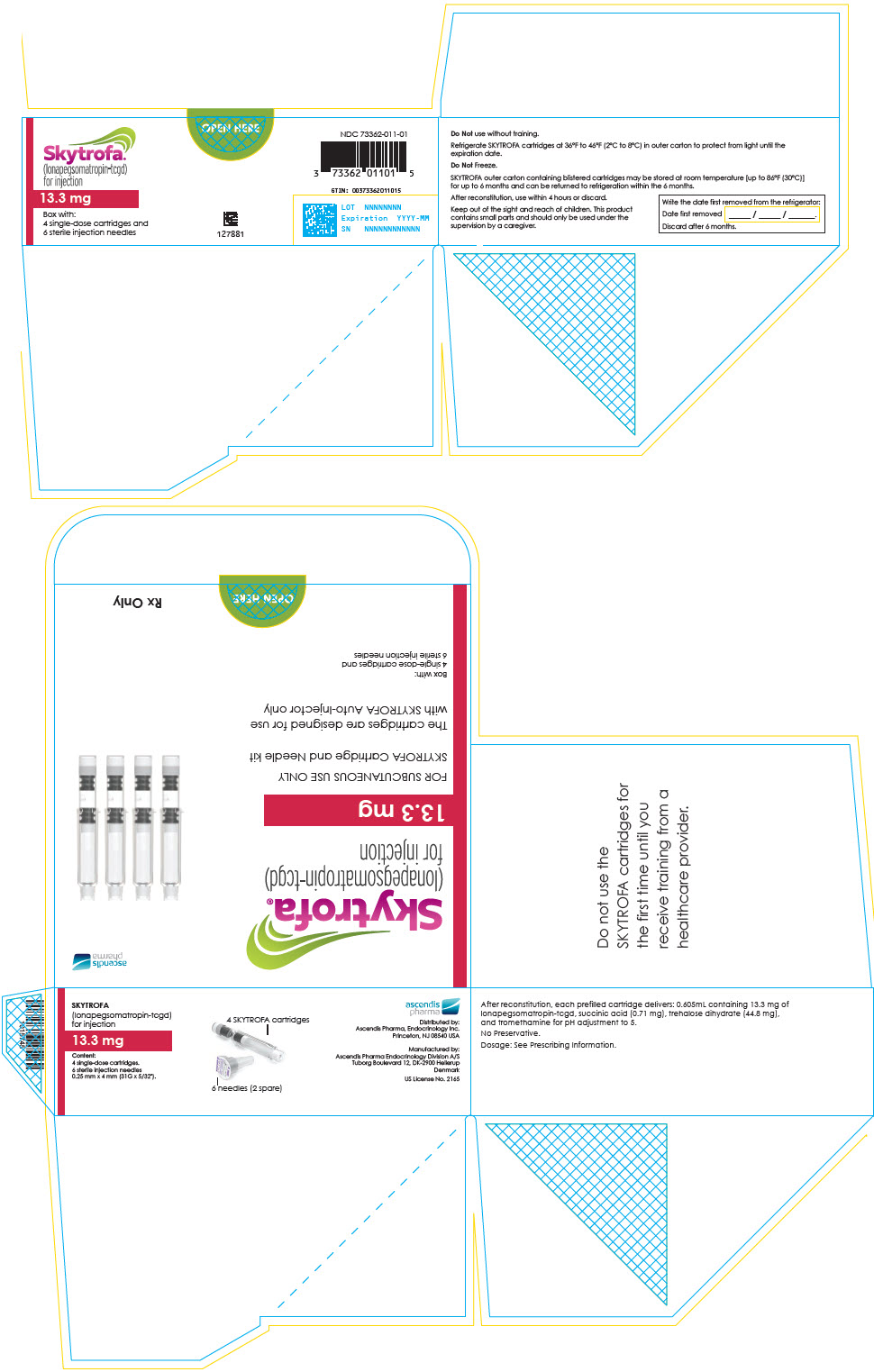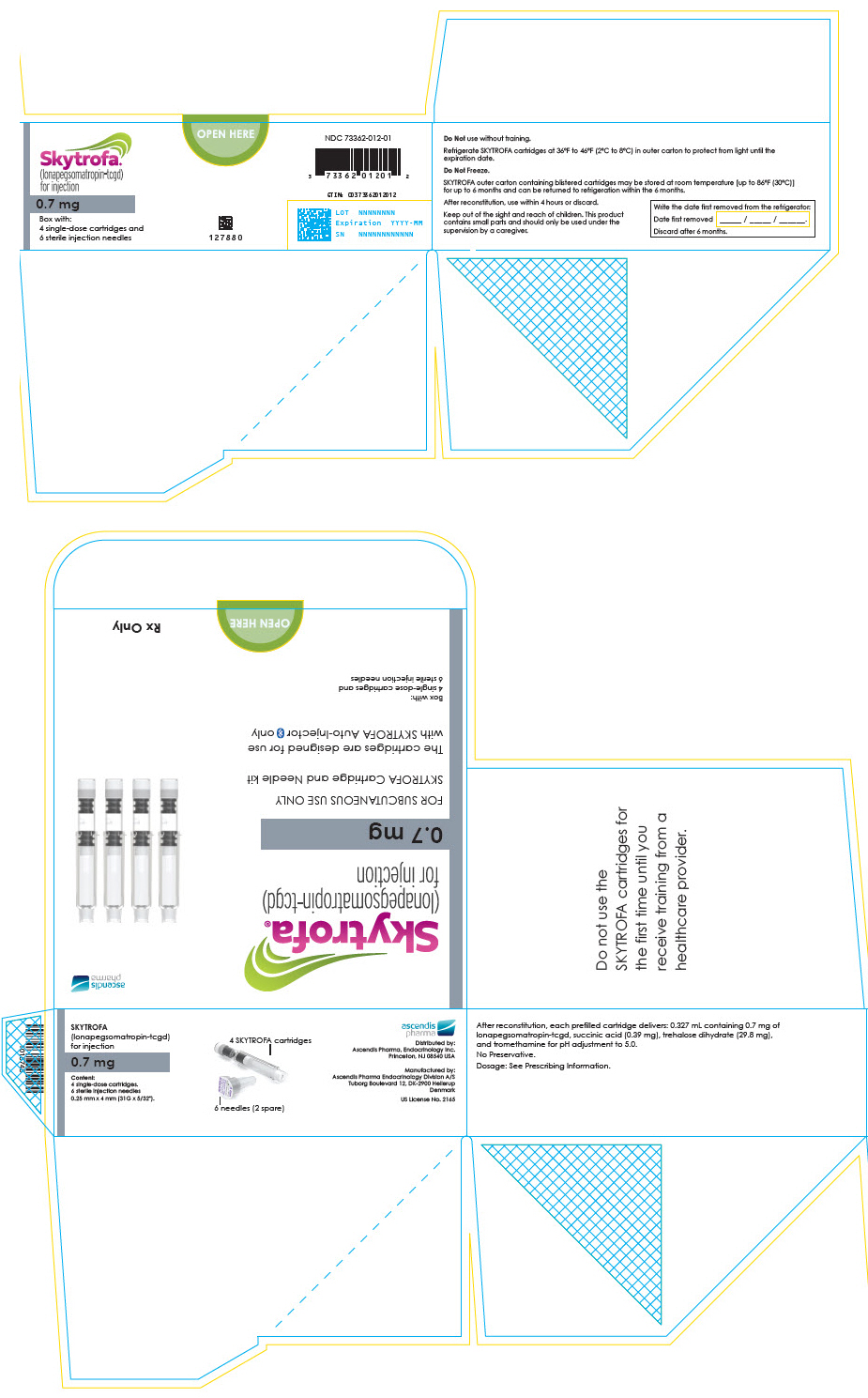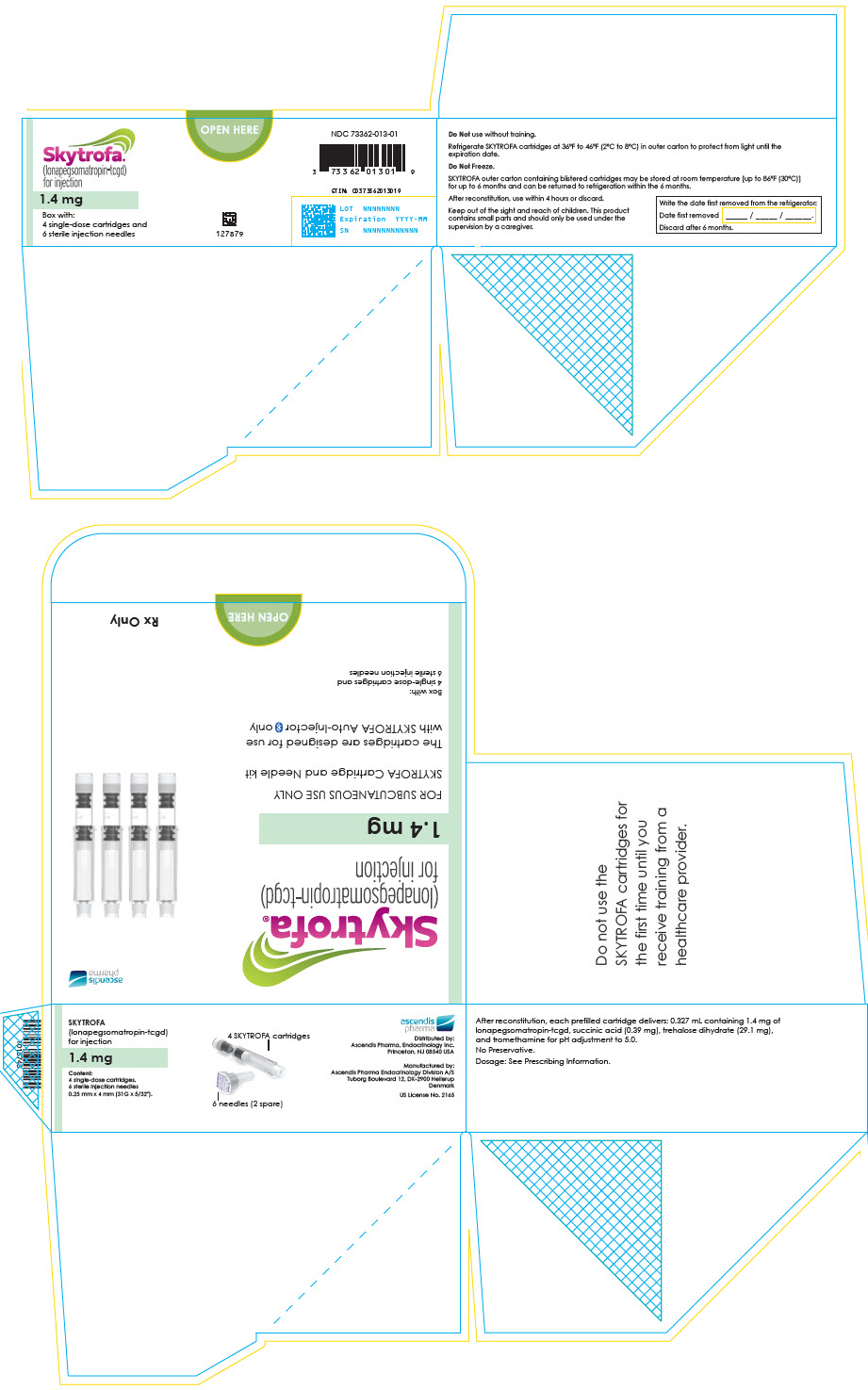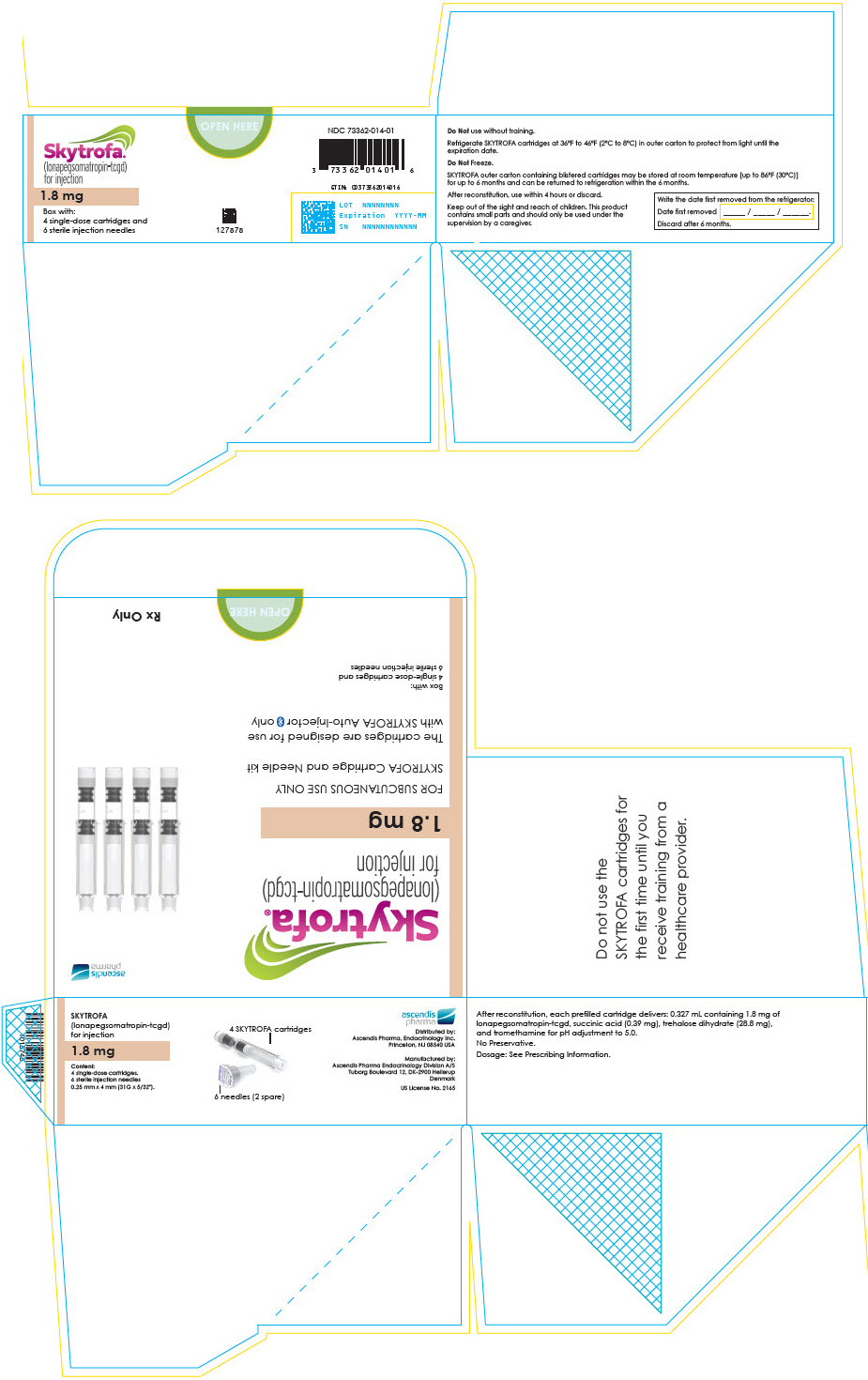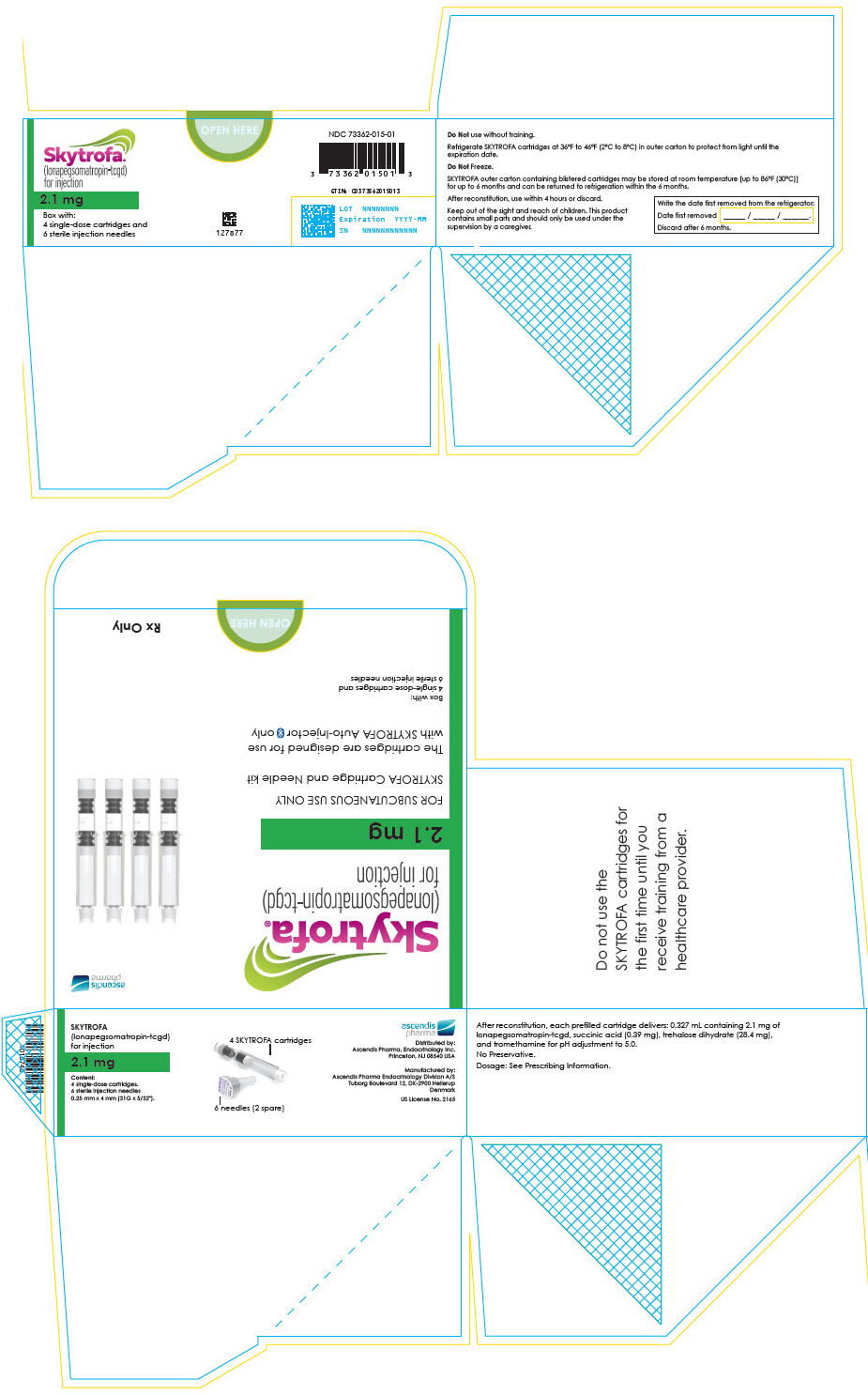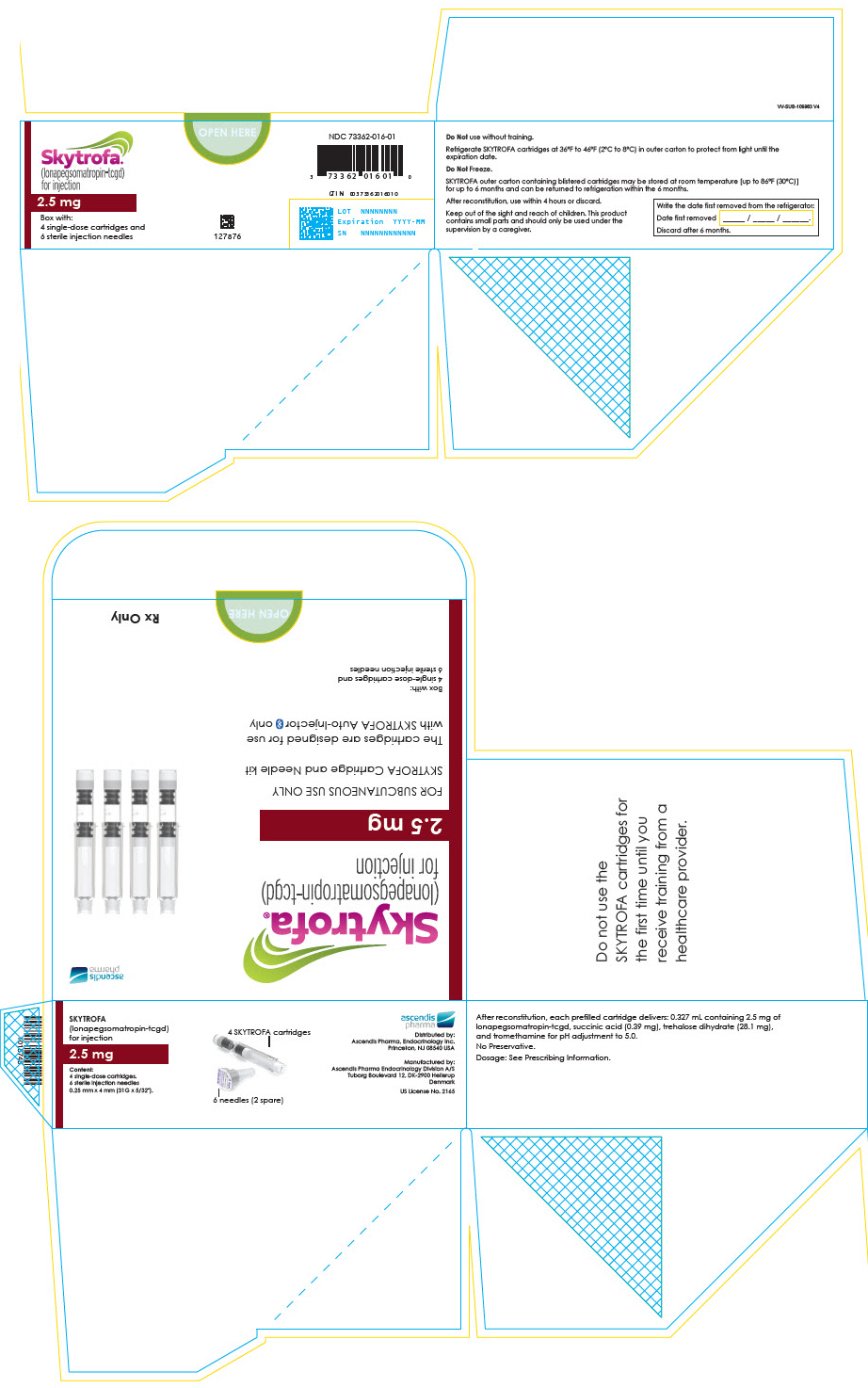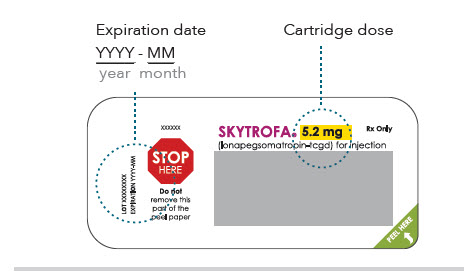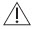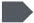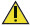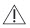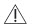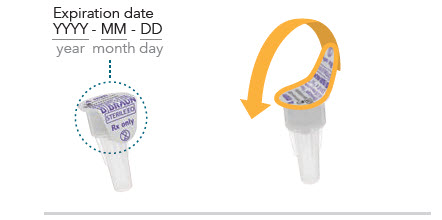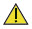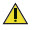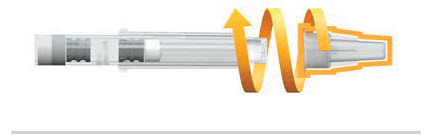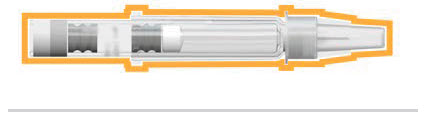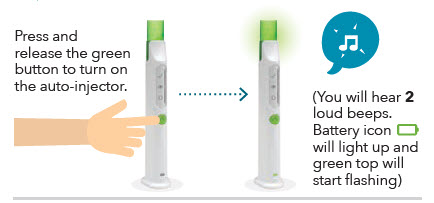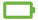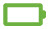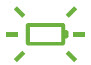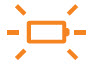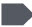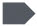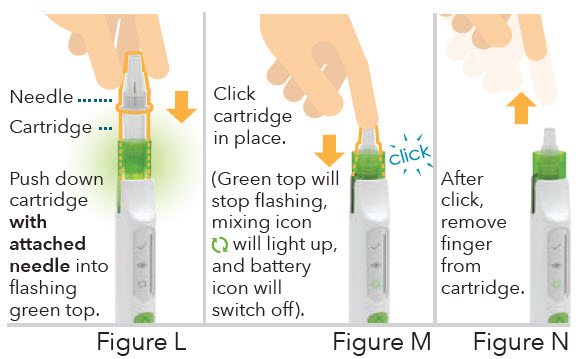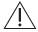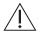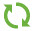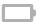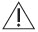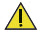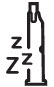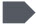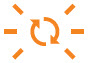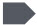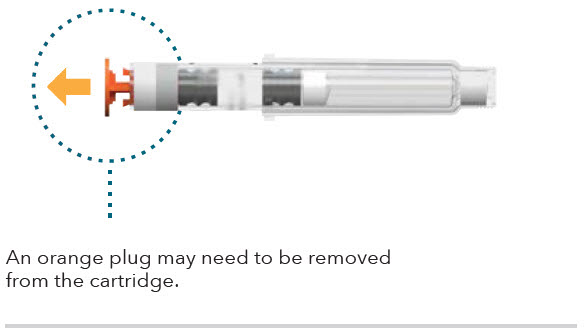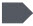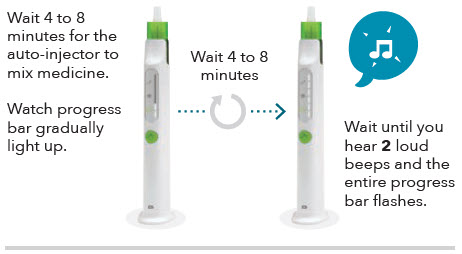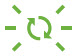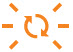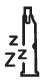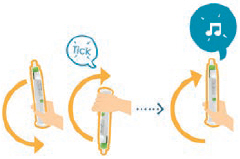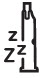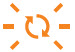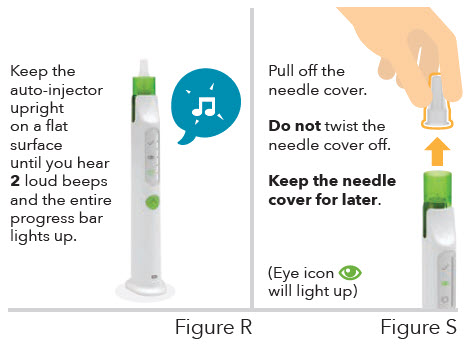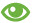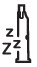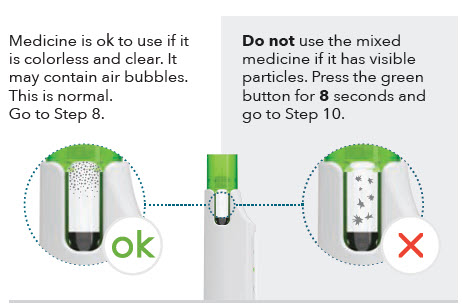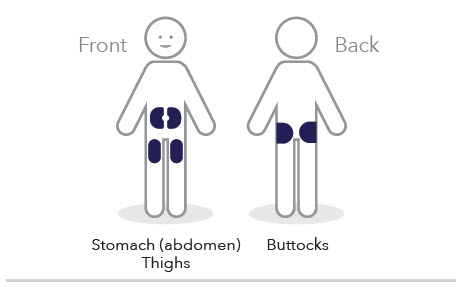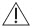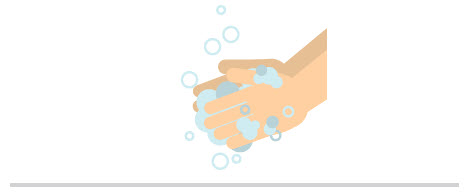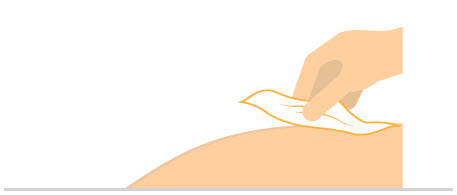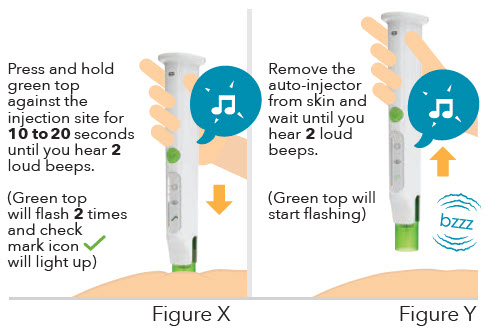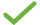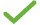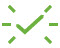 DRUG LABEL: Skytrofa
NDC: 73362-003 | Form: INJECTION, POWDER, LYOPHILIZED, FOR SOLUTION
Manufacturer: Ascendis Pharma Endocrinology, Inc.
Category: prescription | Type: HUMAN PRESCRIPTION DRUG LABEL
Date: 20250904

ACTIVE INGREDIENTS: Lonapegsomatropin 3 mg/1 1

HIGHLIGHTS OF PRESCRIBING INFORMATION

These highlights do not include all the information needed to use SKYTROFA® safely and effectively. See full prescribing information for SKYTROFA®.
SKYTROFA® (lonapegsomatropin-tcgd) for injection, for subcutaneous use
Initial U.S. Approval: 2021

RECENT MAJOR CHANGES

Indications and Usage (1) | 7/2025
Dosage and Administration (2.2, 2.3, 2.6, 2.7) | 7/2025
Warnings and Precautions, Slipped Capital Femoral Epiphysis (5.9) | 7/2025
Warnings and Precautions, Laboratory Tests (5.14) | 7/2025

1 INDICATIONS AND USAGE

SKYTROFA is a human growth hormone indicated for:

- Pediatric Patients: Treatment of pediatric patients 1 year and older who weigh at least 11.5 kg and have growth failure due to inadequate secretion of endogenous growth hormone (GH) (1).
- Adults: Replacement of endogenous growth hormone in adults with growth hormone deficiency (GHD) (1).

2 DOSAGE AND ADMINISTRATION

- SKYTROFA should be administered subcutaneously once weekly into the abdomen, buttock, or thigh with regular rotation of the injection sites (2.7).
- Pediatric Patients: Recommended dose is 0.24 mg/kg body weight once weekly (2.2).
- Adults: Recommended starting dose is based on age and concomitant use of oral estrogen. Titrate monthly until the desired clinical response and/or weekly average IGF-1 concentration are achieved (2.3).
- See Full Prescribing Information for instructions on preparation and administration of drug (2.5, 2.6, 2.7).

3 DOSAGE FORMS AND STRENGTHS

SKYTROFA is a lyophilized powder available in single-dose, dual-chamber, prefilled cartridges containing lonapegsomatropin-tcgd and diluent, Water for Injection, as follows:

For injection: 0.7 mg, 1.4 mg, 1.8 mg, 2.1 mg, 2.5 mg, 3 mg, 3.6 mg, 4.3 mg, 5.2 mg, 6.3 mg, 7.6 mg, 9.1 mg, 11 mg, and 13.3 mg (3)

4 CONTRAINDICATIONS

- Acute critical illness (4)
- Hypersensitivity to somatropin or any of the excipients in SKYTROFA (4)
- Children with closed epiphyses (4)
- Active malignancy (4)
- Active proliferative or severe non-proliferative diabetic retinopathy (4)
- Children with Prader-Willi syndrome who are severely obese or have severe respiratory impairment due to risk of sudden death (4)

5 WARNINGS AND PRECAUTIONS

- Severe Hypersensitivity: Hypersensitivity reactions, including anaphylaxis and angioedema have occurred. In the event of an allergic reaction, seek prompt medical attention (5.2).
- Increased Risk of Neoplasms: Monitor patients with preexisting tumors for progressions or recurrence. Increased risk of a second neoplasm in childhood cancer survivors treated with somatropin – in particular meningiomas in patients treated with radiation to the head for their first neoplasm (5.3).
- Glucose Intolerance and Diabetes Mellitus: May be unmasked. Periodically monitor glucose levels in all patients. Doses of concurrent antihyperglycemic drugs in diabetics may require adjustment (5.4).
- Intracranial Hypertension: Exclude preexisting papilledema. May develop and is usually reversible after discontinuation or dose reduction (5.5).
- Fluid Retention (i.e., edema, arthralgia, carpal tunnel syndrome): May occur. Reduce dose as necessary (5.6).
- Hypoadrenalism: Monitor patients for reduced serum cortisol levels and/or need for glucocorticoid dose increases in those with known hypoadrenalism (5.7).
- Hypothyroidism: May first become evident or worsen (5.8).
- Slipped Capital Femoral Epiphysis in Pediatric Patients: May develop. Evaluate children with the onset of a limp or persistent hip/knee pain (5.9).
- Progression of Preexisting Scoliosis: May develop (5.10).
- Pancreatitis: Consider pancreatitis in patients with persistent severe abdominal pain (5.11).

6 ADVERSE REACTIONS

Pediatric Patients: Most common adverse reactions (≥ 5%): viral infection, pyrexia, cough, nausea and vomiting, hemorrhage, diarrhea, abdominal pain, and arthralgia and arthritis (6.1).

Adults: Most common adverse reaction (≥ 5%): edema peripheral (6.1).

To report SUSPECTED ADVERSE REACTIONS, contact Ascendis Pharma Endocrinology, Inc., at 1-844-442-7236 or FDA at 1-800-FDA-1088 or www.fda.gov/medwatch.

7 DRUG INTERACTIONS

- Replacement Glucocorticoid Treatment: Patients treated with glucocorticoid for hypoadrenalism may require an increase in their maintenance or stress doses following initiation of SKYTROFA (7).
- Pharmacologic Glucocorticoid Therapy and Supraphysiologic Glucocorticoid Treatment: Adjust glucocorticoid dosing in pediatric patients to avoid both hypoadrenalism and an inhibitory effect on growth (7).
- Cytochrome P450-Metabolized Drugs: SKYTROFA may alter the clearance. Monitor carefully if used with SKYTROFA (7).
- Oral Estrogen: Larger doses of SKYTROFA may be required (7).
- Insulin and/or Other Antihyperglycemic Agents: Dose adjustment of insulin or antihyperglycemic agent may be required (7).

FULL PRESCRIBING INFORMATION

1 INDICATIONS AND USAGE

SKYTROFA (lonapegsomatropin-tcgd) is a human growth hormone indicated for the:

- Treatment of pediatric patients 1 year and older who weigh at least 11.5 kg and have growth failure due to inadequate secretion of endogenous growth hormone (GH).
- Replacement of endogenous growth hormone in adults with growth hormone deficiency (GHD).

2 DOSAGE AND ADMINISTRATION

2.1 General Dosing Information

- For subcutaneous injection, once weekly.
- Therapy with SKYTROFA should be supervised by a healthcare provider who is experienced in the diagnosis and management of patients with growth hormone deficiency (GHD).
- Perform fundoscopic examination before initiating treatment with SKYTROFA to exclude preexisting papilledema. If papilledema is identified, evaluate the etiology and treat the underlying cause before initiating treatment with SKYTROFA [see Warnings and Precautions (5.5)].

2.2 Recommended Dosage for Pediatric Patients

- The recommended dose of SKYTROFA for treatment-naïve patients and patients switching from another growth hormone product is 0.24 mg/kg body weight, given once weekly.
- Individualize and titrate the dosage of SKYTROFA based on response.
- When changing from daily somatropin therapy to once-weekly SKYTROFA, wait at least 8 hours between the final dose of daily somatropin and the first dose of SKYTROFA.
- When changing from another once-weekly growth hormone therapy to once-weekly SKYTROFA, wait at least 7 days between the final dose of the previous growth hormone therapy and the first dose of SKYTROFA.
- Assess compliance and evaluate other causes of poor growth, such as hypothyroidism, under-nutrition, advanced bone age and antibodies to recombinant human growth hormone if patients experience failure to increase height velocity, particularly during the first year of treatment.
- Patients who were treated with SKYTROFA for GH deficiency in childhood and whose epiphyses are closed should be reevaluated before continuing SKYTROFA.

2.3 Recommended Dosage for Adults

- The recommended starting dose of SKYTROFA in adults with GHD is based on age and concomitant use of oral estrogen [see Dosage Forms and Strengths (3)]. For treatment-naïve patients or for patients switching from another growth hormone product, start SKYTROFA as described below:
  - 1.4 mg once weekly for adults 30 to 60 years old, with no oral estrogen intake
  - 2.1 mg once weekly for adults under 30 years old, or adults of any age intaking oral estrogen
  - 0.7 mg once weekly for adults over 60 years old, with no oral estrogen intake
- When changing from daily somatropin therapy to once-weekly SKYTROFA, wait at least 8 hours between the final dose of daily somatropin and the first dose of SKYTROFA.
- When changing from another once-weekly growth hormone therapy to once-weekly SKYTROFA, wait at least 7 days between the final dose of the previous growth hormone therapy and the first dose of SKYTROFA.
- Increase the dose monthly to a higher strength cartridge based on the clinical response and/or IGF-1 concentration. Draw IGF-1 serum sample 4 to 5 days after the prior dose.
- Decrease the dose to a lower strength cartridge as needed based on adverse reactions or a weekly average IGF-1 concentration above the age- and sex-specific normal range.
- The maximum recommended dose is 6.3 mg once weekly.

2.4 Missed Doses

- Administer a missed dose as soon as possible and not more than 2 days after the missed dose.
- To avoid missed doses, SKYTROFA can be taken 2 days before or 2 days after the scheduled dosing day. Resume once-weekly dosing for the next dose at the previously scheduled dosing day.
- If more than 2 days have passed from the scheduled day, skip the dose and administer the next dose on the regularly scheduled day.
- At least 5 days should elapse between doses.

2.5 Administration Instructions for Pediatric Patients

SKYTROFA is available in 9 cartridges (dosage strengths in somatropin equivalents) for pediatric patients.

Selection of the appropriate cartridge (mg) is based on the prescribed dose (mg/kg) and the patient's body weight (kg) [see Dosage Forms and Strengths (3)].

- If prescribing a dose of 0.24 mg/kg/week and the patient's weight is 11.5 to 100 kg, follow the recommended dosing in Table 1.
- If prescribing a dose other than 0.24 mg/kg/week, calculate the total weekly dose (in mg) and select the appropriate cartridge as follows:
  - Total weekly dose (mg) = prescribed weekly dose (mg/kg) × patient's body weight (kg).
  - Round the total weekly dose (mg) to the closest cartridge dose while also considering treatment goals and clinical response.

Table 1: Recommended Dosing for Pediatric Patients Prescribed Doses of 0.24 mg/kg/week
Weight (kg) | Dose (mg)
11.5 – 13.9 | 3
14 – 16.4 | 3.6
16.5 – 19.9 | 4.3
20 – 23.9 | 5.2
24 – 28.9 | 6.3
29 – 34.9 | 7.6
35 – 41.9 | 9.1
42 – 50.9 | 11
51 – 60.4 | 13.3
60.5 – 69.9 | 15.2 (using two cartridges of 7.6 mg each)
70 – 84.9 | 18.2 (using two cartridges of 9.1 mg each)
85 – 100 | 22 (using two cartridges of 11 mg each)

2.6 Administration Instructions for Adults

SKYTROFA is available in 14 cartridges (dosage strengths in somatropin equivalents) for adults.

Selection of the appropriate cartridge (mg) is based on the prescribed dose (mg/week) [see Dosage Forms and Strengths (3)].

2.7 Preparation and Administration

- The SKYTROFA cartridge has been designed for use only with the SKYTROFA Auto-Injector.
- If refrigerated, the SKYTROFA cartridge must be kept at room temperature for 15 minutes before use.
- The SKYTROFA Auto-Injector provides a fully automated reconstitution of the lyophilized drug product which is followed by a manual mixing step controlled by the device. When the injection needle is inserted into the skin, the device automatically delivers the drug product. The built-in electronics and software assist the user during the entire preparation and injection sequence and provide confirmation that the full dose has been delivered.
- The mixed solution should be clear and colorless to opalescent. The solution may contain air bubbles and this is acceptable. DO NOT inject if the solution is cloudy or contains particulate matter.
- Use SKYTROFA cartridges within 4 hours after reconstitution. Discard reconstituted SKYTROFA cartridges after 4 hours when stored at room temperature up to 86°F (30°C).
- Inject SKYTROFA subcutaneously into the abdomen, buttock, or thigh. Rotate injection sites between and within regions to reduce the risk of lipoatrophy [see Warnings and Precautions (5.12)].
- Refer to the Instructions for Use for complete administration instructions with illustrations. The instructions can also be found on www.Skytrofa.com/IFU.
- Patients and/or caregivers who will administer SKYTROFA should receive appropriate training and instruction on the proper use of SKYTROFA from their healthcare provider.

3 DOSAGE FORMS AND STRENGTHS

SKYTROFA is a white to off-white lyophilized powder available in a single-dose, dual-chamber, prefilled cartridge containing lonapegsomatropin-tcgd in one chamber and diluent, Water for Injection, in the other chamber and is available in the following strengths:

For injection: 0.7 mg, 1.4 mg, 1.8 mg, 2.1 mg, 2.5 mg, 3 mg, 3.6 mg, 4.3 mg, 5.2 mg, 6.3 mg, 7.6 mg, 9.1 mg, 11 mg, and 13.3 mg.

4 CONTRAINDICATIONS

SKYTROFA is contraindicated in patients with:

- Acute critical illness after open heart surgery, abdominal surgery or multiple accidental trauma, or those with acute respiratory failure due to the risk of increased mortality with use of pharmacologic doses of somatropin [see Warnings and Precautions (5.1)].
- Hypersensitivity to somatropin or any of the excipients in SKYTROFA. Severe systemic hypersensitivity reactions, including anaphylactic reactions and angioedema, have been reported [see Warnings and Precautions (5.2)].
- Pediatric patients with closed epiphyses.
- Active malignancy due to the risk of malignancy progression [see Warnings and Precautions (5.3)].
- Active proliferative or severe non-proliferative diabetic retinopathy because treatment with somatropin may worsen this condition.
- Pediatric patients with Prader-Willi syndrome who are severely obese, have a history of upper airway obstruction or sleep apnea or have severe respiratory impairment due to the risk of sudden death [see Warnings and Precautions (5.13)].

5 WARNINGS AND PRECAUTIONS

5.1 Increased Mortality in Patients With Acute Critical Illness

Increased mortality in patients with acute critical illness due to complications following open heart surgery, abdominal surgery or multiple accidental trauma, or those with acute respiratory failure has been reported after treatment with pharmacologic doses of somatropin [see Contraindications (4)].

The safety of continuing SKYTROFA treatment in patients receiving replacement doses for the approved indication who concurrently develop these illnesses has not been established.

5.2 Severe Hypersensitivity

Severe systemic hypersensitivity reactions, including anaphylactic reactions and angioedema have been reported with postmarketing use of somatropin products, including SKYTROFA. Inform patients and/or caregivers that such reactions are possible, and that prompt medical attention should be sought if an allergic reaction occurs. SKYTROFA is contraindicated in patients with known hypersensitivity to somatropin or any of the excipients in SKYTROFA.

5.3 Increased Risk of Neoplasms

Active Malignancy

There is an increased risk of malignancy progression with somatropin treatment in patients with active malignancy [see Contraindications (4)]. Any preexisting malignancy should be inactive, and its treatment should be completed prior to instituting therapy with SKYTROFA. Discontinue SKYTROFA if there is evidence of recurrent malignancy.

Risk of Second Neoplasm in Pediatric Patients

In childhood cancer survivors who were treated with radiation to the brain/head for their first neoplasm and who developed subsequent growth hormone deficiency (GHD) and were treated with somatropin, an increased risk of a second neoplasm has been reported. Intracranial tumors, in particular meningiomas, were the most common of these second neoplasms. Monitor all patients with a history of GHD secondary to an intracranial neoplasm while on somatropin therapy for progression or recurrence of the tumor.

New Malignancy During Treatment

Because children with certain rare genetic causes of short stature have an increased risk of developing malignancies, thoroughly consider the risks and benefits of starting somatropin in these patients. If treatment with somatropin is initiated, carefully monitor these patients for development of neoplasms.

Monitor patients on SKYTROFA therapy carefully for increased growth or potential malignant changes of preexisting nevi. Advise patients/caregivers to report marked changes in behavior, onset of headaches, vision disturbances and/or changes in skin pigmentation or changes in the appearance of preexisting nevi.

5.4 Glucose Intolerance and Diabetes Mellitus

Treatment with somatropin may decrease insulin sensitivity, particularly at higher doses. Previously undiagnosed impaired glucose tolerance and overt type 2 diabetes mellitus may be unmasked. Monitor glucose levels in all patients receiving SKYTROFA, especially in those with risk factors for type 2 diabetes mellitus, such as obesity or a family history of type 2 diabetes mellitus. When initiating SKYTROFA, monitor closely patients with preexisting type 1 or type 2 diabetes mellitus or impaired glucose tolerance and adjust the doses of antihyperglycemic drugs as needed.

5.5 Intracranial Hypertension

Intracranial hypertension (IH) with papilledema, visual changes, headache, nausea, and/or vomiting has been reported in a small number of patients treated with somatropin. Symptoms usually occurred within 8 weeks after the initiation of somatropin. In all reported cases, IH-associated signs and symptoms resolved rapidly after cessation of therapy or a reduction of the somatropin dose. To exclude preexisting papilledema, perform fundoscopic examination before initiating treatment with SKYTROFA, and reassess periodically thereafter. If papilledema is observed by fundoscopy, stop somatropin treatment. If somatropin-induced IH is confirmed, restart treatment with SKYTROFA at a lower dose after IH-associated signs and symptoms have resolved.

5.6 Fluid Retention

Fluid retention during somatropin therapy may occur. Clinical manifestations of fluid retention (e.g., edema, arthralgia, myalgia, nerve compression syndromes, including carpal tunnel syndrome/paresthesia) are usually transient and dose dependent.

5.7 Hypoadrenalism

Patients receiving somatropin therapy who have or are at risk for pituitary hormone deficiency(s) may be at risk for reduced serum cortisol levels and/or unmasking of central (secondary) hypoadrenalism. In addition, patients treated with glucocorticoid replacement for previously diagnosed hypoadrenalism may require an increase in their maintenance or stress doses following initiation of SKYTROFA therapy. Monitor patients for reduced serum cortisol levels and/or need for glucocorticoid dose increases in patients with known hypoadrenalism [see Drug Interactions (7)].

5.8 Hypothyroidism

Undiagnosed or untreated hypothyroidism may prevent optimal response to SKYTROFA. In patients with GHD, central (secondary) hypothyroidism may first become evident or worsen during SKYTROFA treatment. Therefore, perform periodic thyroid function tests in patients and initiate or appropriately adjust thyroid hormone replacement therapy when indicated.

5.9 Slipped Capital Femoral Epiphysis in Pediatric Patients

Slipped capital femoral epiphysis may occur more frequently in patients undergoing rapid growth. Slipped capital femoral epiphysis may lead to osteonecrosis. Cases of slipped capital femoral epiphysis with or without osteonecrosis have been reported in pediatric patients with short stature receiving somatropin. Evaluate pediatric patients receiving SKYTROFA with the onset of a limp or complaints of persistent hip or knee pain for slipped capital femoral epiphysis and osteonecrosis and manage accordingly.

5.10 Progression of Preexisting Scoliosis in Pediatric Patients

Somatropin increases growth rate in pediatric patients, and progression of existing scoliosis can occur in patients who experience rapid growth. Somatropin has not been shown to increase the occurrence of scoliosis. Monitor patients with a history of scoliosis for disease progression.

5.11 Pancreatitis

Pancreatitis has been reported in pediatric patients receiving somatropin. The risk may be greater in pediatric patients than adults. Consider pancreatitis in patients who develop persistent severe abdominal pain.

5.12 Lipoatrophy

When SKYTROFA is administered subcutaneously at the same site over a long period of time, lipoatrophy may result. Rotate injection sites when administering SKYTROFA to reduce this risk [see Dosage and Administration (2.7)].

5.13 Sudden Death in Pediatric Patients With Prader-Willi Syndrome

There have been reports of fatalities after initiating therapy with somatropin in pediatric patients with Prader-Willi syndrome who had one or more of the following risk factors: severe obesity, history of upper airway obstruction or sleep apnea, or unidentified respiratory infection. Male patients with one or more of these factors may be at greater risk than females. SKYTROFA is not indicated for the treatment of pediatric patients who have growth failure due to genetically confirmed Prader-Willi syndrome.

5.14 Laboratory Tests

Serum levels of alkaline phosphatase and phosphate may increase after SKYTROFA therapy. Serum levels of parathyroid hormone may increase after somatropin treatment. If a patient is found to have abnormal laboratory tests, monitor as appropriate.

6 ADVERSE REACTIONS

The following important adverse reactions are described elsewhere in the labeling:

- Increased mortality in patients with acute critical illness [see Warnings and Precautions (5.1)]
- Severe hypersensitivity [see Warnings and Precautions (5.2)]
- Increased risk of neoplasms [see Warnings and Precautions (5.3)]
- Glucose intolerance and diabetes mellitus [see Warnings and Precautions (5.4)]
- Intracranial hypertension [see Warnings and Precautions (5.5)]
- Fluid retention [see Warnings and Precautions (5.6)]
- Hypoadrenalism [see Warnings and Precautions (5.7)]
- Hypothyroidism [see Warnings and Precautions (5.8)]
- Slipped capital femoral epiphysis in pediatric patients [see Warnings and Precautions (5.9)]
- Progression of preexisting scoliosis in pediatric patients [see Warnings and Precautions (5.10)]
- Pancreatitis [see Warnings and Precautions (5.11)]
- Lipoatrophy [see Warnings and Precautions (5.12)]
- Sudden death in pediatric patients with Prader-Willi syndrome [see Warnings and Precautions (5.13)]

6.1 Clinical Trials Experience

Because clinical trials are conducted under widely varying conditions, adverse reaction rates observed in the clinical trials of a drug cannot be directly compared to rates in the clinical studies of another drug and may not reflect the rates observed in clinical practice.

Pediatric Patients with Growth Hormone Deficiency

SKYTROFA was studied in a 52-week, open-label, active-controlled trial in 161 treatment-naïve, prepubertal pediatric patients with growth hormone deficiency (GHD) [see Clinical Studies (14.1)]. The subjects ranged in age from 3.2 to 13.1 years with a mean of 8.5 years. One hundred thirty-two (82%) of the subjects were male and 29 (18%) were female. One subject was Asian, 3 were Black or African American, 152 were Caucasian, and 5 were categorized as "other."

Table 2 shows common adverse reactions that occurred in ≥ 5% of patients treated with SKYTROFA in this trial.

Table 2: Adverse Reactions Occurring in ≥ 5% SKYTROFA-Treated Pediatric Patients and More Frequently Than in Daily Somatropin-Treated Pediatric Patients (52 Weeks of Treatment)
Adverse reactions | Daily Somatropin (N = 56) n (%) | SKYTROFA (N = 105) n (%)
Infection, viral | 6 (11%) | 16 (15%)
Pyrexia | 5 (9%) | 16 (15%)
Cough | 4 (7%) | 11 (11%)
Nausea and vomiting | 4 (7%) | 11 (11%)
Hemorrhage [Hemorrhage in the SKYTROFA treatment group included epistaxis (3), contusion (2), petechiae (1) and eye hemorrhage (1).] | 1 (2%) | 7 (7%)
Diarrhea | 3 (5%) | 6 (6%)
Abdominal pain | 2 (4%) | 6 (6%)
Arthralgia and arthritis [Arthralgia and arthritis in the SKYTROFA treatment group included arthralgia (5) and reactive arthritis (1).] | 1 (2%) | 6 (6%)
Adverse reactions that are medically related were grouped to a single preferred term.

Laboratory Tests

More SKYTROFA-treated patients shifted from normal baseline levels to elevated phosphate and alkaline phosphatase levels at the end of the trial compared to the daily somatropin group (44.2% vs. 30.2% and 19.2% vs. 9.4%, respectively); these laboratory changes occurred intermittently [see Warnings and Precautions (5.14)].

Adults with Growth Hormone Deficiency

SKYTROFA was studied in a 38-week parallel-arm, placebo-controlled (double-blind) and active-controlled (open label) trial in 259 adults with growth hormone deficiency (GHD) [see Clinical Studies (14.2)].

The mean (range) age at enrollment was 43 (23 to 81) years old, with 119 (46%) females (55 on oral estrogen) and 140 (54%) males. One subject was American Indian or Alaska Native, one was Black or African American, 28 were Asian, and 218 were Caucasian.

Table 3 shows adverse reactions that occurred in ≥ 5% of adults treated with SKYTROFA and more frequently than in placebo-treated adults in this trial.

Table 3: Adverse Reactions Occurring in ≥ 5% of SKYTROFA-Treated Adults and More Frequently Than in Placebo-treated Adults (38 Weeks of Treatment)
Adverse reactions | Placebo (N = 84) n (%) | SKYTROFA (N = 89) n (%)
Edema [Edema in the SKYTROFA treatment group included edema peripheral (6) and peripheral swelling (1).] | 1 (1%) | 7 (8%)
Central (secondary) hypothyroidism [Central (secondary) hypothyroidism in the SKYTROFA treatment group included thyroxine free decreased (3), central hypothyroidism (2), thyroxine decreased (1), blood thyroid stimulating hormone decreased (1), tri-iodothyronine free decreased (1). Preexisting central hypothyroidism in 5 of 6 SKYTROFA-treated patients.] | 1 (1%) | 6 (7%)
Adverse reactions that are medically related were grouped to a single preferred term.

Laboratory Tests

More SKYTROFA-treated patients shifted from normal or low baseline levels to elevated alkaline phosphatase levels at the end of the trial compared to the placebo group (14% vs. 6%); these laboratory changes were noted with increased frequency as the trial progressed [see Warnings and Precautions (5.14)].

6.2 Postmarketing Experience

The following adverse reactions have been identified during post approval use of somatropin products or SKYTROFA. Because these reactions are reported voluntarily from a population of uncertain size, it is not always possible to reliably estimate their frequency or establish a causal relationship to drug exposure.

- Severe systemic hypersensitivity reactions, including anaphylactic reactions and angioedema
- Musculoskeletal and connective tissue disorders – osteonecrosis in pediatric patients

7 DRUG INTERACTIONS

Table 4 includes a list of drugs with clinically important drug interactions when administered concomitantly with SKYTROFA and instructions for preventing or managing them.

Table 4: Clinically Important Drug Interactions with SKYTROFA
Replacement Glucocorticoid Treatment
Clinical Impact: | Microsomal enzyme 11β-hydroxysteroid dehydrogenase type 1 (11βHSD-1) is required for conversion of cortisone to its active metabolite, cortisol, in hepatic and adipose tissue. Somatropin inhibits 11βHSD-1. Consequently, individuals with untreated growth hormone deficiency (GHD) have relative increases in 11βHSD-1 and serum cortisol. Initiation of SKYTROFA may result in inhibition of 11βHSD-1 and reduced serum cortisol concentrations.
Intervention: | Patients treated with glucocorticoid replacement for hypoadrenalism may require an increase in their maintenance or stress doses following initiation of SKYTROFA [see Warnings and Precautions (5.7)]
Examples | Cortisone acetate and prednisone may be affected more than others because conversion of these drugs to their biologically active metabolites is dependent on the activity of 11βHSD-1.
Pharmacologic Glucocorticoid Therapy and Supraphysiologic Glucocorticoid Treatment
Clinical Impact: | Pharmacologic glucocorticoid therapy and supraphysiologic glucocorticoid treatment may attenuate the growth-promoting effects of SKYTROFA in pediatric patients.
Intervention: | Carefully adjust glucocorticoid replacement dosing in pediatric patients receiving glucocorticoid treatments to avoid both hypoadrenalism and an inhibitory effect on growth.
Cytochrome P450-Metabolized Drugs
Clinical Impact: | Limited published data indicate that somatropin treatment increases cytochrome P450 (CYP450)-mediated antipyrine clearance. SKYTROFA may alter the clearance of compounds known to be metabolized by CYP450 liver enzymes.
Intervention: | Careful monitoring is advisable when SKYTROFA is administered in combination with drugs metabolized by CYP450 liver enzymes.
Oral Estrogen
Clinical Impact: | Oral estrogens may reduce the serum insulin-like growth factor-1 (IGF-1) response to SKYTROFA.
Intervention: | Patients receiving oral estrogen replacement may require higher SKYTROFA dosages.
Insulin and/or Other Antihyperglycemic Agents
Clinical Impact: | Treatment with SKYTROFA may decrease insulin sensitivity, particularly at higher doses.
Intervention: | Patients with diabetes mellitus may require adjustment of their doses of insulin and/or other antihyperglycemic agents [see Warnings and Precautions (5.4)].

8 USE IN SPECIFIC POPULATIONS

8.1 Pregnancy

Risk Summary

There are no available data on lonapegsomatropin-tcgd use in pregnant patients to evaluate a drug-associated risk of major birth defects, miscarriage or adverse maternal or fetal outcomes. Available published data over several decades for somatropin, the active component of lonapegsomatropin-tcgd, have not identified a drug-associated risk of major birth defects, miscarriage or adverse maternal or fetal outcomes. In animal reproduction studies, there was no evidence of embryo-fetal or neonatal harm when pregnant rats were administered subcutaneous lonapegsomatropin-tcgd at doses up to 13-fold the clinical pediatric dose of 0.24 mg/kg/week and approximately 30-fold the maximum clinical therapeutic dose for adult GHD of 6.3 mg hGH/week (see Data).

The estimated background risk of birth defects and miscarriages for the indicated population is unknown. All pregnancies have a background risk of birth defect, loss, or other adverse outcomes. In the U.S. general population, the estimated background risk of major birth defects and miscarriages in clinically recognized pregnancies is 2% to 4% and 15% to 20%, respectively.

Data

Animal Data

No embryonic or fetal development toxicities occurred in rats administered subcutaneous lonapegsomatropin-tcgd at doses up to 13-fold the clinical pediatric dose of 0.24 mg/kg/week and approximately 30-fold the maximum clinical therapeutic dose for adult GHD of 6.3 mg hGH/week.

In a peri- and post-natal developmental study in rats, there were no adverse effects on the pregnant/lactating female or on development of the conceptus and the offspring following exposure of the female from implantation through weaning to doses of a structurally related pegylated somatropin prodrug up to 13-fold the clinical pediatric dose of 0.24 mg/kg/week and approximately 30-fold the maximum clinical therapeutic dose for adult GHD of 6.3 mg hGH/week.

8.2 Lactation

Risk Summary

There are no data on the presence of lonapegsomatropin-tcgd in human milk, effects on the breastfed infant, or effects on milk production. High molecular weight therapeutic proteins, including lonapegsomatropin-tcgd, are expected to have low passage into human milk and limited systemic exposure in the breastfed infant. Additionally, published data indicate that exogenous somatropin does not increase normal human milk concentrations of growth hormone. No adverse effects on the breastfed infant have been reported with somatropin. The developmental and health benefits of breastfeeding should be considered along with the mother's clinical need for SKYTROFA and any potential adverse effects on the breastfed infant from SKYTROFA or from the underlying maternal condition.

8.4 Pediatric Use

Safety and effectiveness of SKYTROFA have been established in pediatric patients 1 year and older and who weigh at least 11.5 kg. Pediatric use was established in a controlled study of 161 treatment-naïve pediatric patients ages 3 to 13 years and by supportive data in pediatric patients 1 year and older [see Adverse Reactions (6) and Clinical Studies (14)].

The safety and effectiveness of SKYTROFA in children less than 1 year of age have not been established.

Use of somatropin in pediatric patients with Prader-Willi syndrome has been associated with reports of sudden death. SKYTROFA is not indicated for the treatment of pediatric patients with growth failure due to genetically confirmed Prader-Willi syndrome [see Warnings and Precautions (5.13)].

8.5 Geriatric Use

Of the 249 patients who received SKYTROFA in clinical studies, 24 (10%) patients were 65 years of age and older, and 4 (2%) patients were 75 years of age and older. Geriatric patients may be at an increased risk for adverse reactions. Initiate SKYTROFA at 0.7 mg once weekly in patients 60 years of age and older, not on estrogen therapy [see Dosage and Administration (2.3)].

9 DRUG ABUSE AND DEPENDENCE

9.1 Controlled Substance

SKYTROFA is a prodrug of somatropin. Somatropin is not a controlled substance.

9.2 Abuse

Inappropriate use of somatropin may result in significant negative health consequences.

9.3 Dependence

Somatropin is not associated with drug related withdrawal adverse reactions.

10 OVERDOSAGE

Acute overdosage may lead initially to hypoglycemia and subsequently to hyperglycemia. Overdose with somatropin may cause fluid retention. Long-term overdosage may result in signs and symptoms of gigantism consistent with the known effects of excess growth hormone.

11 DESCRIPTION

Lonapegsomatropin-tcgd is a long-acting prodrug of a human growth hormone (somatropin) produced by recombinant DNA technology using E. coli. Lonapegsomatropin-tcgd consists of a parent drug, somatropin, that is conjugated to a methoxypolyethylene glycol carrier (4 × 10 kDa mPEG) via a proprietary TransCon Linker and has a molecular weight of 63 kDa (released somatropin is 22 kDa). In vitro assay confirms the minimum potency of released somatropin is NLT 2.5 IU/mg.

SKYTROFA (lonapegsomatropin-tcgd) for injection is a sterile, preservative-free, white to off-white lyophilized powder available in a single-dose, dual-chamber, prefilled cartridge containing lonapegsomatropin-tcgd in one chamber and the diluent, Water for Injection, in the other chamber. SKYTROFA prefilled cartridge must be used with SKYTROFA Auto-Injector to provide an automatic mixing step for reconstitution prior to subcutaneous use.

After reconstitution, each prefilled cartridge delivers:

- 0.327 mL containing 0.7 mg lonapegsomatropin-tcgd, succinic acid (0.39 mg), trehalose dihydrate (29.8 mg) and tromethamine for pH adjustment to 5.0.
- 0.327 mL containing 1.4 mg lonapegsomatropin-tcgd, succinic acid (0.39 mg) trehalose dihydrate (29.1 mg) and tromethamine for pH adjustment to 5.0.
- 0.327 mL containing 1.8 mg lonapegsomatropin-tcgd, succinic acid (0.39 mg) trehalose dihydrate (28.8 mg) and tromethamine for pH adjustment to 5.0.
- 0.327 mL containing 2.1 mg lonapegsomatropin-tcgd, succinic acid (0.39 mg) trehalose dihydrate (28.4 mg) and tromethamine for pH adjustment to 5.0.
- 0.327 mL containing 2.5 mg lonapegsomatropin-tcgd, succinic acid (0.39 mg) trehalose dihydrate (28.1 mg) and tromethamine for pH adjustment to 5.0.
- 0.273 mL containing 3 mg lonapegsomatropin-tcgd, succinic acid (0.32 mg), trehalose dihydrate (22.7 mg) and tromethamine for pH adjustment to 5.0.
- 0.327 mL containing 3.6 mg lonapegsomatropin-tcgd, succinic acid (0.39 mg), trehalose dihydrate (27.1 mg) and tromethamine for pH adjustment to 5.0.
- 0.391 mL containing 4.3 mg lonapegsomatropin-tcgd, succinic acid (0.46 mg) and trehalose dihydrate (32.5 mg) and tromethamine for pH adjustment to 5.0.
- 0.473 mL containing 5.2 mg lonapegsomatropin-tcgd, succinic acid (0.56 mg) and trehalose dihydrate (39.3 mg) and tromethamine for pH adjustment to 5.0.
- 0.286 mL containing 6.3 mg lonapegsomatropin-tcgd, succinic acid (0.34 mg) and trehalose dihydrate (21.2 mg) and tromethamine for pH adjustment to 5.0.
- 0.345 mL containing 7.6 mg lonapegsomatropin-tcgd, succinic acid (0.41 mg) and trehalose dihydrate (25.5 mg) and tromethamine for pH adjustment to 5.0.
- 0.414 mL containing 9.1 mg lonapegsomatropin-tcgd, succinic acid (0.49 mg) and trehalose dihydrate (30.6 mg) and tromethamine for pH adjustment to 5.0.
- 0.5 mL containing 11 mg lonapegsomatropin-tcgd, succinic acid (0.59 mg) and trehalose dihydrate (37 mg) and tromethamine for pH adjustment to 5.0.
- 0.605 mL containing 13.3 mg lonapegsomatropin-tcgd, succinic acid (0.71 mg) and trehalose dihydrate (44.8 mg) and tromethamine for pH adjustment to 5.0.

12 CLINICAL PHARMACOLOGY

12.1 Mechanism of Action

SKYTROFA is a pegylated human growth hormone (somatropin) for once-weekly subcutaneous injection [see Clinical Pharmacology (12.3)].

Somatropin binds to the growth hormone (GH) receptor in the cell membrane of target cells resulting in intracellular signal transduction and a host of pharmacodynamic effects. Somatropin has direct tissue and metabolic effects, and indirect effects mediated by insulin-like growth factor-1 (IGF-1), including stimulation of chondrocyte differentiation and proliferation, stimulation of hepatic glucose output, protein synthesis and lipolysis. Somatropin stimulates skeletal growth in pediatric patients with growth hormone deficiency (GHD) as a result of effects on the growth plates (epiphyses) of long bones.

12.2 Pharmacodynamics

Somatropin released from SKYTROFA produces a linear IGF-1 dose response. In pediatric patients with GHD, with a dose change of 0.02 mg/kg/week on average resulting in a mean change in weekly average IGF-1 standard deviation score (SDS) of 0.17. In adults with GHD, a dose change of 1 mg/week results in a mean change in weekly average IGF-1 SDS of 0.7 (range, 0.3 to 1.2).

At steady state, IGF-1 levels peak approximately 2 days post-dose, with the weekly average IGF-1 occurring approximately 4.5 days post-dose. IGF-1 levels are in the normal range for GHD patients for the majority of the week, similar to daily somatropin.

12.3 Pharmacokinetics

Absorption

Following subcutaneous dose administration, SKYTROFA releases fully active somatropin via autocleavage of the TransCon linker that follows first-order kinetics.

In pediatric patients with GHD, following subcutaneous dose administration of 0.24 mg/kg/week SKYTROFA, the observed mean (CV%) steady-state peak serum concentration (Cmax) of lonapegsomatropin-tcgd was 1230 (86.3) ng hGH/mL, and the median time to reach maximum concentrations (Tmax) was 25 hours. For released somatropin, Cmax was 15.2 (83.4) ng/mL with a median Tmax of 12 hours. The mean (CV%) somatropin exposure over the one-week dose interval (area under the curve) was 500 (83.8) h*ng/mL. Following subcutaneous dose administration of 0.24 mg/kg/week SKYTROFA, mean Cmax (CV%) of the methoxypolyethylene glycol carrier was 13.1 (28.1) mcg/mL with a median Tmax of 36 hours.

In adult patients with GHD, following subcutaneous administration of 6.3 mg/week SKYTROFA, the estimated median steady-state Cmax of lonapegsomatropin-tcgd was 69.3 ng hGH/mL, and the Tmax was 31 hours. For released somatropin, the estimated median Cmax was 2.47 ng/mL with a median Tmax of 13 hours. The median somatropin exposure over the one-week dose interval (area under the curve) was 75.4 h*ng/mL. Following subcutaneous dose administration of 6.3 mg/week SKYTROFA, the estimated median Cmax of the methoxypolyethylene glycol carrier was 4.60 mcg/mL with a median Tmax of 34 hours.

No significant accumulation of lonapegsomatropin-tcgd and somatropin following repeat dose administration was observed.

Distribution

In pediatric patients with GHD, the mean (CV%) steady-state apparent volume of distribution of lonapegsomatropin-tcgd after subcutaneous administration of 0.24 mg/kg/week SKYTROFA was 0.13 (109) L/kg.

In adult patients with GHD, the median steady-state apparent volume of distribution of lonapegsomatropin-tcgd after subcutaneous administration of 6.3 mg/week SKYTROFA was 0.13 L/kg.

A similar distribution pattern as observed for daily somatropin is expected once somatropin is released from lonapegsomatropin-tcgd.

Elimination

Metabolism

The metabolism of somatropin involves protein catabolism in both the liver and kidneys. The methoxypolyethylene glycol carrier is cleared by the kidneys.

Excretion

In pediatric patients with GHD, the mean (CV%) lonapegsomatropin-tcgd apparent clearance at steady state was 3.2 (67) mL/h/kg following subcutaneous administration of 0.24 mg/kg/week SKYTROFA with a mean (±SD) observed half-life of 30.7 (±12.7) hours.

The apparent half-life of somatropin released from lonapegsomatropin-tcgd was approximately 25 hours.

Specific Populations

Based on a population pharmacokinetic analysis, age (3.0 to 13.7 years for pediatric patients and 23 to 75 years for adult patients), sex, race, and body weight do not have clinically meaningful effects on pharmacokinetics.

Male and Female Patients — No sex-specific pharmacokinetic studies have been performed with SKYTROFA. The available literature indicates that the pharmacokinetics of somatropin are similar in men and women.

Patients with Renal or Hepatic Impairment — No specific studies have been performed with SKYTROFA.

12.6 Immunogenicity

The observed incidence of anti-drug antibodies is highly dependent on the sensitivity and specificity of the assay. Differences in assay methods preclude meaningful comparisons of the incidence of anti-drug antibodies in the studies described below with the incidence of anti-drug antibodies in other studies, including those of SKYTROFA or other growth hormone products.

Anti-lonapegsomatropin-tcgd antibodies were evaluated in samples collected every 3 months in phase 3 trials in pediatric patients with GHD receiving SKYTROFA. Mean duration of exposure to SKYTROFA was 70.2 weeks. Of the 304 patients with post-baseline assessments, 19 (6.3%) showed detectable binding antibodies to lonapegsomatropin-tcgd. No apparent correlation of anti-lonapegsomatropin-tcgd antibodies to adverse events or loss of efficacy was observed. No neutralizing antibodies to SKYTROFA were detected.

Of the 247 adult patients with GHD, treated with SKYTROFA and with post-baseline assessments, antibodies against lonapegsomatropin-tcgd were detected in 14 patients (5.7%, mean duration of exposure was 47.7 weeks). There was no identified clinically significant effect of anti-lonapegsomatropin-tcgd antibodies on the safety and efficacy of SKYTROFA. No neutralizing antibodies to SKYTROFA were detected.

13 NONCLINICAL TOXICOLOGY

13.1 Carcinogenicity, Mutagenesis, Impairment of Fertility

Carcinogenicity studies have not been conducted with lonapegsomatropin-tcgd.

Lonapegsomatropin-tcgd was not mutagenic in the Ames test, in the human chromosomal aberration assay or in the rat bone marrow micronucleus test.

In an animal fertility study, lonapegsomatropin-tcgd was administered via subcutaneous injection to male and female rats before cohabitation, through mating to implantation.

Lonapegsomatropin-tcgd did not affect fertility or early embryo-fetal development at doses up to 20-fold the clinical pediatric dose of 0.24 mg/kg/week and approximately 46-fold the maximum clinical therapeutic dose for adult GHD of 6.3 mg hGH/week.

14 CLINICAL STUDIES

14.1 Treatment-Naïve Pediatric Patients With Growth Hormone Deficiency (NCT02781727)

A multi-center randomized, open-label, active-controlled, parallel-group phase 3 study was conducted in 161 treatment-naïve, prepubertal pediatric subjects with growth hormone deficiency (GHD); 105 subjects received once-weekly SKYTROFA, and 56 received daily somatropin. The dose in both arms was 0.24 mg/kg/week. The primary efficacy endpoint was annualized height velocity at Week 52.

The subjects ranged in age from 3.2 to 13.1 years with a mean of 8.5 years. One hundred thirty-two (82%) subjects were male and 29 (18%) were female. One subject was Asian, three were Black or African American, 152 were Caucasian, and five were categorized as "other." The subjects had a mean baseline height SDS (standard deviation score) of -2.9.

Treatment with once-weekly SKYTROFA for 52 weeks resulted in an annualized height velocity of 11.2 cm/year. Subjects treated with daily somatropin achieved an annualized height velocity of 10.3 cm/year after 52 weeks of treatment. Refer to Table 5.

Table 5: Annualized Height Velocity at Week 52 in Pediatric Treatment-Naïve Subjects with Growth Hormone Deficiency
 | Once-Weekly SKYTROFA (N = 105) | Daily Somatropin (N = 56) | Estimate of Treatment Difference (95% CI) (SKYTROFA minus Daily Somatropin)
Annualized Height Velocity (cm/year) [The estimates of least squares (LS) means and 95% confidence interval (CI) are from an ANCOVA model that included baseline age, peak GH levels (log transformed) at stimulation test, baseline height SDS – average SDS of parental height as covariates, and treatment and sex as factors. Missing data were imputed with multiple imputation method.] | 11.2 | 10.3 | 0.9 (0.2-1.5)

Height SDS (change from baseline) was 1.1 in the SKYTROFA arm and 0.96 in the daily somatropin arm at Week 52. Refer to Table 6.

Table 6: Height SDS over 52 Weeks in Pediatric Treatment-Naïve Subjects with Growth Hormone Deficiency
 | Once-Weekly SKYTROFA (N = 105) | Daily Somatropin (N = 56)
Height SDS, baseline | -2.9 | -3.0
Height SDS, change from baseline [Height SDS, change from baseline: The estimates of LS means are from an ANCOVA model that included baseline age, peak GH levels (log transformed) at stimulation test and baseline height SDS as covariates, and treatment and sex as factors.] | 1.1 | 0.96
Abbreviations: SDS, standard deviation score.

14.2 Adults With Growth Hormone Deficiency (NCT05171855)

A multi-center, randomized, parallel-group, placebo-controlled (double-blind), phase 3 study was conducted in 259 adults with GHD. Eighty-nine subjects received once-weekly SKYTROFA, 84 subjects received once-weekly placebo, and 86 subjects received open-label daily somatropin.

The mean (range) age at enrollment was 43 (23 to 81) years old, with 119 (46%) females (55 on oral estrogen) and 140 (54%) males, and the (SD) baseline body mass index of 28 (6.3) kg/m^2. One subject was American Indian or Alaska Native, 1 was Black or African American, 28 were Asian, and 218 were Caucasian.

The primary efficacy endpoint, change in trunk percent (%) fat was measured by dual X-ray absorptiometry from baseline to Week 38 in the SKYTROFA group, compared to the placebo group (see Table 7).

Table 7: Change in Trunk Percent Fat from Baseline After 38 Weeks of Treatment in Adults with Growth Hormone Deficiency – SKYTROFA vs. Placebo
Change from Baseline at Week 38 | Once-Weekly SKYTROFA (N = 89) | Once-Weekly Placebo (N = 84) | LS Mean Difference [95% CI] | P-value
Trunk percent fat (%) [The estimates of least squares (LS) means and 95% confidence interval (CI) are from an ANCOVA model that included treatment arm, region (North America, Europe, Asia-Pacific), baseline age group, gender, concomitant oral estrogen at screening (yes vs. no), and adult GHD onset (adult vs. childhood) and corresponding baseline variable as a covariate. Missing data were imputed with multiple imputation method.] | -1.7 | 0.4 | -2.0 [-2.9, -1.1] | < 0.0001
Abbreviations: LS, least squares; CI, confidence interval; kg, kilogram.

Patients treated with daily somatropin achieved a change in trunk percent fat of -3.1% after 38 weeks. No formal statistical comparison between SKYTROFA and daily somatropin was conducted.

Change in total body lean mass and trunk fat mass from baseline after 38 weeks of treatment were secondary efficacy endpoints.

At 38 weeks, the change from baseline in total body lean mass was +1.6 kg for lonapegsomatropin and -0.1 kg for placebo (LS mean difference of 1.7 kg with 95% CI of 1.0 to 2.5, p-value < 0.0001).

At 38 weeks, the change from baseline in trunk fat mass was -0.5 kg for lonapegsomatropin and +0.2 kg for placebo (LS mean difference of -0.7 kg with 95% CI of -1.2 to -0.2, p-value = 0.005).

After 38 weeks, SKYTROFA treatment in adults with GHD resulted in normalization of IGF-1 SDS to 1.4 compared to -2.6 in placebo-treated patients. See Table 8.

Table 8: IGF-1 SDS at Baseline and after 38 Weeks of Treatment in Adults with Growth Hormone Deficiency – SKYTROFA vs. Placebo
Time Point | Once-Weekly SKYTROFA (N = 89) | Once-Weekly Placebo (N = 84)
Baseline IGF-1 SDS, mean (SD) | -2.6 (1.0) | -2.7 (1.2)
Week 38 IGF-1 SDS, mean (SD) [Sampling time corresponded to weekly average IGF-1 SDS for SKYTROFA.] | 1.4 (1.9) | -2.6 (1.3)
Abbreviations: SD, standard deviation; SDS, standard deviation score.

The mean (SD) IGF-1 SDS level in daily somatropin treated patients was -2.82 (1) at baseline and 0.49 (1.98) at 38 weeks. No formal statistical comparison between SKYTROFA and daily somatropin was conducted.

16 HOW SUPPLIED/STORAGE AND HANDLING

How Supplied

SKYTROFA (lonapegsomatropin-tcgd) for injection is a sterile, preservative-free, white to off-white lyophilized powder available in a single-dose, dual-chamber, prefilled cartridge containing lonapegsomatropin-tcgd in one chamber and the diluent, Water for Injection, in the second chamber. The dual-chamber glass cartridge is available in 14 strengths (in somatropin equivalents) as described in Table 9.

Table 9: SKYTROFA Presentations
SKYTROFA | NDC
0.7 mg | 73362-012-01
1.4 mg | 73362-013-01
1.8 mg | 73362-014-01
2.1 mg | 73362-015-01
2.5 mg | 73362-016-01
3 mg | 73362-003-01
3.6 mg | 73362-004-01
4.3 mg | 73362-005-01
5.2 mg | 73362-006-01
6.3 mg | 73362-007-01
7.6 mg | 73362-008-01
9.1 mg | 73362-009-01
11 mg | 73362-010-01
13.3 mg | 73362-011-01

Each carton contains 4 single-dose prefilled cartridges and 6 sterile, single-use, disposable 0.25 mm × 4 mm (31-gauge × 5/32 inch) needles. The cartridges are for use only with the SKYTROFA Auto-Injector, packaged in a separate carton. The SKYTROFA Auto-Injector is not supplied with SKYTROFA cartridges but is available for patients with a prescription for SKYTROFA through the Ascendis Pharma Customer Support by calling the toll-free number at 1-844-442-7236 (1-844-44ASCENDIS).

Storage and Handling

- For patients: Refrigerate SKYTROFA cartridges at 36°F to 46°F (2°C to 8°C) in the outer carton to protect from light until the expiration date. Do not freeze. Alternatively, SKYTROFA outer carton containing blistered cartridges may be stored at room temperature [up to 86°F (30°C)] for up to 6 months and can be returned to refrigeration within the 6 months. Write the date first removed from the refrigerator in the space provided on the outer carton. Do not use SKYTROFA beyond the expiration date or 6 months after the date it was first removed from refrigeration (whichever is earlier).
- For pharmacy long-term storage: Store SKYTROFA cartridges refrigerated at 36°F to 46°F (2°C to 8°C) in the outer carton to protect from light until the expiration date. Do not freeze.

17 PATIENT COUNSELING INFORMATION

Administration Instructions

- Advise patients and/or caregivers to read the accompanying FDA-approved patient labeling SKYTROFA Auto-Injector Instructions for Use (also available at www.Skytrofa.com/IFU) prior to administration. Advise patients and/or caregivers to call the Ascendis Pharma Customer Support toll-free number at 1-844-442-7236 (1-844-44ASCENDIS) for assistance or additional training, if needed.
- Advise patients and/or caregivers to refer to the Instructions for Use that accompanies the SKYTROFA Auto-Injector for complete mixing and administration instructions with illustrations [see Dosage and Administration (2.7)]. Instruct patients and/or caregivers of proper needle disposal and caution against any reuse of needles. An appropriate container for the disposal of used cartridge and needle should be used.
- Advise patients and/or caregivers to administer SKYTROFA once weekly, at any time of day. Advise patients and/or caregivers that doses can be taken 2 days before or 2 days after the scheduled dosing day. Advise patients and/or caregivers to resume once-weekly dosing for the next dose. If more than 2 days have passed from the schedule dosing day, advise patients and/or caregivers to skip the missed dose and take the next dose on the regularly scheduled day. If subsequently changing the regular dosing day to a different day of the week, advise patients and/or caregivers to ensure that at least 5 days will elapse between the last dose and the newly established regular dosing day.

Hypersensitivity Reactions

Advise patients and/or caregivers that severe and/or serious systemic hypersensitivity reactions (anaphylaxis and angioedema) have been reported, and to seek prompt medical attention should an allergic reaction occur [see Warnings and Precautions (5.2)].

Neoplasms

Advise childhood cancer survivors and/or caregivers that individuals treated with brain and/or head radiation are at increased risk of secondary neoplasms and, as a precaution, need to be monitored for recurrence. Advise patients and/or caregivers to report marked changes in behavior, onset of headaches, vision disturbances and/or changes in skin pigmentation or changes in the appearance of preexisting nevi.

Glucose Intolerance/Diabetes Mellitus

Advise patients and/or caregivers that new onset impaired glucose intolerance/type 2 diabetes mellitus or exacerbation of preexisting diabetes mellitus can occur and monitoring of blood glucose during treatment with SKYTROFA may be needed.

Intracranial Hypertension

Advise patients and/or caregivers to report to their healthcare provider any visual changes, headache, and nausea and/or vomiting.

Fluid Retention

Advise patients and/or caregivers that fluid retention during SKYTROFA replacement therapy may occur. Inform patients and/or caregivers of the clinical manifestations of fluid retention (e.g., edema, arthralgia, myalgia, nerve compression syndromes, including carpal tunnel syndrome/paresthesia) and to report to their healthcare provider if any of these signs or symptoms occur during treatment with SKYTROFA.

Hypoadrenalism

Advise patients and/or caregivers that patients who have or who are at risk for pituitary hormone deficiency(s) that hypoadrenalism may develop and to report to their healthcare provider if they experience hyperpigmentation, extreme fatigue, dizziness, weakness, or weight loss.

Hypothyroidism

Advise patients and/or caregivers that undiagnosed/untreated hypothyroidism may prevent an optimal response to SKYTROFA. Advise patients/caregivers that patients may require periodic thyroid function tests.

Pancreatitis

Advise patients and/or caregivers that pancreatitis may develop and to report to their healthcare provider any new onset abdominal pain.

© 2024 Ascendis Pharma. All rights reserved. SKYTROFA®, Ascendis®, TransCon®, the Ascendis Pharma logo and the company logo are trademarks owned by the Ascendis Pharma Group.

PATENT INFORMATION: www.ascendispharma.us/products/patents

Manufactured by:
Ascendis Pharma Endocrinology Division A/S
Tuborg Boulevard 12 Hellerup Denmark DK-2900
U.S. License Number 2165

For information about SKYTROFA contact:
Ascendis Pharma Endocrinology, Inc.
Princeton, New Jersey 08540, USA
1-844-442-7236 (1-844-44ASCENDIS)
www.Skytrofa.com

INSTRUCTIONS FOR USE

Keep Track of Your Injections

This is your
Instructions for Use

Instructions
for Use

- Important Information
- Before You Begin
- Setting Up

- Step-by-Step Guide

- Troubleshooting
- Cleaning and Maintenance
- Charging and Charging Cable
- Storing

- Product Safety
- Expiration
- EMC Compliance Levels
- Technical Specification
- Symbols
- Warranty and Disclaimer
- Parts Overview

Introduction

Intended Purpose and Device Description:

The SKYTROFA Auto-Injector is intended to automate the mixing (reconstitution) and injection under the skin (subcutaneous use) of lonapegsomatropin in patients prescribed one-time weekly growth hormone therapy.

Injections are given under the skin (subcutaneously) one-time weekly in the abdomen, thighs, or buttocks.

The intended users are patients prescribed with SKYTROFA, caregivers, and healthcare providers.

Always use SKYTROFA exactly as your healthcare provider has told you. If you are unsure about your medicine, contact your healthcare provider.

Consult your healthcare provider to be advised to perform self-administration or administration by your caregiver.

The auto-injector is an electromechanical, reusable, single-patient use, and single-dose delivery device designed for personal home use. This means that a patient or caregiver can give injections at home without a healthcare provider present.

A healthcare provider can use the auto-injector in a non-emergency clinical setting to inject a patient or demonstrate device use.

Contraindications and Side Effects

For more information on SKYTROFA contraindications, side effects, disease, self-care, summary of safety, and clinical performance, please refer to the information enclosed with your medicine or contact your healthcare provider.

If you get any side effects, contact your healthcare provider.

Step-by-step Instructions for the SKYTROFA Auto-Injector

Read and follow this Instructions for Use that comes with your auto-injector before you start using it. This information does not replace talking to your healthcare provider about your medical condition or your treatment.

The back cover of this Instructions for Use folds out for reference while you read the rest of the instructions.

If you have any questions about the auto-injector, the medicine, or these instructions, please contact your healthcare provider or Ascendis Pharma Customer Support. For contact information back cover.

Getting Started

Page
Important Information | 6
Before You Begin | 9
Setting Up | 12

Important Information

Important information about your SKYTROFA Auto-Injector:

Do not use the SKYTROFA Auto-Injector for the first time until you receive training from a healthcare provider. Follow this Instructions for Use for the auto-injector to avoid getting an injury, infection, or incorrect dose.

The auto-injector can only be used with SKYTROFA Cartridges and needles that are prescribed by your healthcare provider. Cartridges and needles come together in the same packaging. Follow the instructions that come with SKYTROFA Cartridges. If refrigerated, take the cartridge out of the refrigerator and leave at room temperature for 15 minutes before use.

Do not use your auto-injector with other medicines or needles than provided in the SKYTROFA Cartridge pack.

Your weekly dose may require that you use 2 cartridges.

When this warning symbol is seen, safety instructions must be followed. Otherwise, serious safety hazardous situations and injuries may occur.

Do not share your auto-injector with other people, even if the needle has been changed. You may give other people a serious infection or get a serious infection from them.

Keep out of the reach of children.
This product contains small parts that may present a choking hazard to small children. The cable can present a strangulation hazard.

Do not use any charger or charging cables other than those included with your auto-injector. Read more on page 65.

Do not use or place the auto-injector closer than 12 inches (30 cm) to microwave ovens or electronic equipment with antennas such as Wi-Fi transceivers. The auto-injector might not work the right way.

When this precaution symbol is seen, safety instructions must be followed. Otherwise, safety hazardous situations and injuries and potential damage to the auto-injector or other property may occur.

Do not reuse needles.

Do not use a cartridge if it has been dropped or you think it may be damaged.

Do not point the auto-injector at yourself or other people, except when you are ready to inject, to avoid needle stick injury.

If your auto-injector turns off automatically, press and release the green button to turn it on again and read page 60 to proceed.

If the auto-injector packaging has been damaged or unintentionally opened before first using it, please call Ascendis Pharma Customer Support. For contact information back cover.

Before You Begin

The SKYTROFA Auto-Injector

Your healthcare provider will inform you that the SKYTROFA Auto-Injector, which comes in a separate package, is required for injecting the prescribed the SKYTROFA medicine.

The SKYTROFA Auto-Injector is exclusively for use with SKYTROFA Cartridge (medicine).

The SKYTROFA Auto-Injector automates part of the procedure for injecting SKYTROFA medicine.

The SKYTROFA Cartridge

The medicine SKYTROFA comes in a one-time use cartridge "SKYTROFA Cartridge". The cartridge has 2 chambers, 1 filled with powder and 1 filled with water. The auto-injector automatically mixes the powder and the water during mixing steps, making it ready for injection. Each SKYTROFA Cartridge pack contains 4 cartridges packed in individual blisters.

The Needle

The single-use needle comes with SKYTROFA Cartridges and is used for screwing on the cartridge to inject the medicine. Each SKYTROFA Cartridge pack contains 6 needles including 2 spare needles.

Contact your healthcare provider if you need more SKYTROFA consumables.

Figure A

Product Overview

Figure B

Setting Up

1. Remove the SKYTROFA Auto-Injector from the package.
  - Use the auto-injector at room temperature between 59°F to 86°F (15°C to 30°C).
2. Connect the USB (large end of the cable) to the charger (only use the provided charger). Plug the charger into a power outlet. Connect the Micro-USB (small end of the cable) to the back of the auto-injector. For protection, charge the auto-injector with the protective cover on (see Figure C).
  - For more information on charging page 65.
    Figure C
3. Fully charge the auto-injector before using it for the first time. This will take 2 hours and 30 minutes. When the battery icon located at the base of the auto-injector (see Figure D) is flashing orange or green, it is charging. When it shows constant green, the auto-injector is fully charged and is ready to use after the charging cable is unplugged.
  - When fully charged, the battery should last for at least 3 injections.
  - When traveling, bring regional adaptors for the auto-injector charger to connect to the local power outlet.
  - The auto-injector cannot be used when connected to the charger.
    Figure D
4. Find a quiet place where you can perform your injection.
5. Gather your supplies and place them on a flat, hard, clean surface.
  Supplies needed for an injection:
  From SKYTROFA Auto-Injector packaging
  (see Figure B):
  - 1 SKYTROFA Auto-Injector
  From SKYTROFA Cartridge pack
  (see Figure E):
  - 1 SKYTROFA Cartridge
  - 1 Omnican fine 0.25 mm × 4 mm (31G × 5/32") B. Braun needle
  Other supplies (not included)
  (see Figure E):
  - 1 Alcohol Wipe
  - 1 Sharps Container

If your weekly dose requires 2 cartridges, you will need the following additional supplies:

- 1 SKYTROFA Cartridge
- 1 Omnican fine 0.25 mm × 4 mm (31G × 5/32") B. Braun needle
- 1 Alcohol Wipe

Supplies Needed for Each Injection

Figure E

Does Your Weekly Dose Require 2 Cartridges?

Your healthcare provider may prescribe a dose that requires use of the medicine in 2 cartridges.
If you have been prescribed a dose that requires 2 cartridges:

- Take your first injection (Step 1 to Step 11, pages 20–47).
- Then take your second injection by repeating Step 1 to Step 11 with a new cartridge and needle.
- After your second injection, continue to Step 12 (page 48).

Figure F

How to Use

Step-by-Step Guide | Page
Prepare | 20
Mix | 30
Inject | 38
After Injection | 44

Prepare

1 Check and assemble cartridge and needle

Figure G

1.1

Check the expiration date and cartridge dose on the cartridge packaging (see Figure G).

Do not use if the dose is not as prescribed.

Remove the SKYTROFA Cartridge from the packaging according to the instructions on its lid.

If refrigerated, take the cartridge out of the refrigerator and leave at room temperature for 15 minutes before use.

Do not use if the expiration date has passed on the cartridge.

- If you are unsure about your dose, contact your healthcare provider.
- If you are unsure about the medicine expiration date, please call Ascendis Pharma Customer Support. For contact information back cover.

1.2

Check the expiration date on the needle. Peel off the paper from the needle by hand (see Figure H).

Be careful with the exposed needle to avoid needle stick injury and infection.

Do not use the needle if:

- The protective paper is broken, not fully sealed, or not removed by hand.
- The expiration date has passed.

Do not use a bent needle.
Figure H

1.3

Screw the needle straight on the cartridge by turning clockwise until there is a tight fit (see Figure I and J).

Do not remove the plastic needle cover. You will need it to insert the cartridge into the SKYTROFA Auto-Injector. Check the needle is screwed tight on the cartridge.

Do not use the needle if it has touched anything other than the injection site.

Figure I

Check the needle is screwed tight on the cartridge (see Figure J).

Figure J

2 Turn on the auto-injector

Figure K

2.1

Disconnect the auto-injector from the charger when charged.

- The auto-injector cannot be used when connected to the charger.

2.2

Find a quiet place where you can give your injection. Use the auto-injector at room temperature between 59°F to 86°F (15°C to 30°C).

2.3

Remove the protective cover. Place the auto-injector upright on a flat surface.

2.4

Press and release the green button to turn on the auto-injector (see Figure K).

- You will hear a humming sound. The battery icon and the 3 icons above the green button will light up. Then all of the icons will turn off, except the battery icon.
- You will hear 2 loud beeps and the green top will start flashing. The auto-injector is ready for use.
- If the auto-injector is not active for 6 minutes, it will turn off. Press the green button to turn it on again.

2.5

Check the battery icon on the base of the auto-injector to see if it is charged. The battery icon is green when the auto-injector is ready to use:

Constant Green
Battery is fully charged.
The auto-injector is ready to use.

Flashing Green
At least 1 injection remaining, but charging is recommended after use.

Flashing Orange
Battery needs charging.

If no icons light up page 56.

If you see flashing icons (other than the battery) pages 58–59.

3 Insert cartridge with attached needle

3.1

Insert the cartridge.

Insert the cartridge into the flashing green top by pushing straight down with the needle cover still on (see Figure L).

3.2

Click the cartridge into place.

Make sure the cartridge is pushed all the way down until you hear a click (see Figure M).

- You will hear a click, the green top will stop flashing, the green mixing icon will light up, and the battery icon will switch off.

Do not insert the cartridge without attaching the needle fully. If you did not attach the needle, push the cartridge to release it and continue with Step 1.2 (page 21).

Do not attempt to insert the charging cable in the auto-injector if a cartridge has been inserted.

3.3

After the click, remove your finger from the cartridge (see Figure N).

- You will hear a repeating notification sound if the auto-injector is not standing upright. Keep the auto-injector standing upright on a flat surface.

If your auto-injector turns off automatically, press and release the green button to turn it on again, then read Situation A page 61.

If you see a flashing orange mixing icon page 58.
If you cannot insert the cartridge, check if an orange plug is still attached to the cartridge. If an orange plug is still attached to the cartridge, remove it by pulling it straight off (see Figure O). The orange plug only protects the cartridge during transportation.

Figure O

Do not use the auto-injector if you cannot insert the cartridge. Please call Ascendis Pharma Customer Support. For contact information back cover.

Mix

4 Wait while mixing
Figure P
4.1 | Wait 4 to 8 minutes for the auto-injector to mix your medicine. The progress bar will gradually light up, and you will hear steady ticking during mixing (see Figure P).; - Make sure the auto-injector is standing upright on a flat surface. If the auto-injector is not upright, the medicine mixing will pause.
 | If you see a slowly flashing green mixing icon and the progress bar is frozen page 54.
 | If you see a flashing orange mixing icon page 58.
4.2 | The auto-injector has finished the automatic part of the mixing when you hear 2 loud beeps and the entire progress bar flashes.
4.3 | Continue with Step 5 (page 32) immediately after automatic mixing is completed. If you wait for more than 2 hours before completing the steps for mixing the medicine by hand (Step 5), the auto-injector will automatically cancel the procedure. If this happens, the cartridge will be released and cannot be used. To remove the cartridge, see Step 10 (page 44). If you still need to inject after the auto-injector has canceled the procedure, go back to Step 1 and use a new cartridge (page 20).
 | If your auto-injector turns off automatically, press and release the green button to turn it on again, then read Situation B page 61.

5 Turn the auto-injector up and down

Turn the auto-injector up and down, listening for a tick sound each up and down cycle to make sure the turns are correct.

Turn up and down correctly 5 to 10 times until you hear 2 loud beeps and the whole progress bar, except the top element, lights up.

Do not press the green button.

Figure Q

5.1 | Turn the auto-injector up and down to mix the medicine by hand. You will hear a 'tick' sound each time you turn the auto-injector up and down correctly. To mix the medicine correctly:; - Each turn up and down should take no more than 2 seconds, followed by a tick sound. - The auto-injector should point straight down and straight up (see Figure Q).; The progress bar, except the top element, will light up as you turn the auto-injector up and down correctly. Do not press the green button. Pressing and holding the green button for 8 seconds will cancel mixing, and you cannot reuse the cartridge. After 5 to 10 correct turns, you will hear 2 loud beeps and the progress bar, except the top element, will light up.
 | If your auto-injector turns off automatically, press and release the green button to turn it on again. Read Situation B or C to find the corresponding lit-up icons page 61 and 62.
 | If you see a flashing orange mixing icon page 58.
5.2 | Continue with Step 6 (page 36) immediately after you finish mixing by hand. If you wait more than 2 hours before performing Step 6 to Step 9 (pages 36–43), the auto-injector will automatically cancel the procedure. If this happens, the cartridge will be released and cannot be used. To remove the cartridge, see Step 10 (page 44).; - If you still need to inject after the auto-injector has canceled the procedure, go back to Step 1 and use a new cartridge (page 20).

6 Finish mixing

6.1

Keep the auto-injector upright for automatic air removal (see Figure R). Wait until you hear 2 loud beeps and the entire progress bar lights up.

If you see a slowly flashing green mixing icon and the progress bar is frozen page 54.

If you see a flashing orange mixing icon page 58.

6.2

Pull off the needle cover (see Figure S). The green eye icon will light up. Removing the needle cover will allow you to check the mixed medicine in the inspection window (Step 7 on page 38).
Do not twist the needle cover off. If you have trouble removing the needle cover, gently pull up the green top.

Keep the needle cover for later use. It is needed to safely remove the cartridge after injection.

If your auto-injector turns off automatically, press and release the green button to turn it on again. Read Situation D or E to find the corresponding lit-up icons page 62 and 63.

Inject

7 Check mixed medicine

Figure T

7.1

Check the mixed medicine in the inspection window on the side of the auto-injector (see Figure T).
The medicine should look colorless and clear. It may contain air bubbles. This is normal.

Be careful with the exposed needle to avoid needle stick injury and infection.
Do not inject the medicine if there are visible particles (medicine is not dissolved) or the mixed medicine is discolored.
If you see visible particles or the medicine is discolored:

- Cancel the injection procedure by pressing and holding the green button for 8 seconds. This will unlock the cartridge. Go to Step 10 (page 44).
- Get a new cartridge. Follow the instructions beginning at Step 1 (page 20).

If you see a flashing orange mixing icon page 58.

8 Prepare for injection

Figure U

8.1

Choose an injection site.

There are only 3 areas of your body you can inject into (see Figure U):

- Stomach (abdomen)
- Thighs
- Buttocks

Change the injection site for every injection.

8.2

Make sure your hands are clean using soap and water or hand sanitizer (see Figure V).

Figure V

8.3

Clean the injection site with an alcohol wipe (see Figure W).

Do not inject in an injection site that has not been cleaned.

Do not touch the cleaned area before injecting.

Do not fan or blow on the cleaned area.

Inject directly into skin. Do not inject through clothes.

Figure W

9 Inject medicine

9.1

Press and hold the green top against the skin of the injection site to inject (see Figure X). Hold for 10 to 20 seconds until you hear 2 loud beeps and the green top flashes 2 times. The green check mark icon will light up.

- The medicine is injected automatically when you press the green top against the skin.
- You will hear steady ticking and the progress bar will light up as you inject.

Do not remove the auto-injector from the injection site until the injection is finished to ensure you get your full cartridge dose.
The injection is finished when you hear 2 loud beeps and the green top flashes 2 times. The green check mark will light up.

9.2

Remove the auto-injector from the skin after the injection is finished (see Figure Y).

- After the injection is finished, the auto-injector makes a buzzing sound as it unlocks the cartridge. Wait until you hear 2 loud beeps, and the green top starts to flash.

If you see a slowly flashing green check mark icon and the progress bar is frozen page 55.

If you see a flashing orange check mark icon page 58.

After Injection

10 Remove cartridge

Be careful when handling needles to reduce the risk of needlestick injury and infection.

10.1

Press down the needle cover into the flashing green top until you hear a click to remove the cartridge (see Figure Z).

- You will hear a click and see the green top stop flashing (see Figure Z).

Do not twist the cartridge.

10.2

Remove the used cartridge by pulling straight up (see Figure AA).

Do not remove the cartridge without using the needle cover.

- After you remove the cartridge, the battery icon will display the battery level. The auto-injector turns off automatically.

Do not use the auto-injector if you cannot remove the cartridge as instructed. Please call Ascendis Pharma Customer Support. For contact information back cover.

11 Check cartridge and throw away

Figure AB

11.1

Check that the cartridge is empty of medicine (see Figure AB).

Do not use the auto-injector if there is medicine left in the cartridge after injection. Please call Ascendis Pharma Customer Support. For contact information back cover.

11.2

Put your used cartridge and needle in an FDA-cleared sharps disposal container right away after use (see Figure AB).

Do not throw away (dispose of) opened or used needles and cartridges in your household trash.
Do not recycle your used sharps disposal container.
If you do not have an FDA-cleared sharps disposal container, you may use a household container that is:

- Made of a heavy-duty plastic
- Can be closed with a tight-fitting, puncture-resistant lid without sharps being able to come out
- Upright and stable during use
- Leak-resistant
- Properly labeled to warn of hazardous waste inside the container

When your sharps disposal container is almost full, you will need to follow your community guidelines for the right way to dispose of your sharps disposal container. There may be state or local laws about how to throw away used needles and syringes. For more information about safe sharps disposal, go to the FDA's website at: http://www.fda.gov/safesharpsdisposal.

Healthcare providers, relatives, and other caregivers should follow this Instructions for Use for removal and throwing away (disposal) of needles to prevent needlestick injury and infection.

Does Your Weekly Dose Require 2 Cartridges?
Then take the second injection by repeating Step 1 to Step 11 (pages 20–47) with a new cartridge and needle before continuing to Step 12.

12 Store the auto-injector

Figure AC

12.1

Make sure that the auto-injector is clean. If it is dirty or if medicine has been spilled onto it, clean with a damp cloth and wait until dry.
Do not place the auto-injector under water. For more information on cleaning page 64.

12.2

Put the protective cover on the auto-injector by sliding it straight down (see Figure AC).

12.3

Charge the auto-injector if the battery icon has been flashing before or after the injection. For more information about how to charge the auto-injector page 65.

12.4

It is recommended to store the auto-injector at room temperature between 59°F to 86°F (15°C to 30°C), in between uses. Store with the protective cover on until the next injection. For more information about how to store the auto-injector page 66.

12.5

Write down the date of every weekly dose taken under Keep Track of Your Injections back cover fold out.

- When the auto-injector reaches its expiration date, maximum number of injections, or needs replacing, return it to the Ascendis Pharma Customer Support. For more information, see Expiration page 72.

Troubleshooting and Care

 | Page
Troubleshooting | 52
Cleaning and Maintenance | 64
Charging and Charging Cable | 65
Storing | 66

Troubleshooting

- What do you see?

Orange flashing icons
If you see any of these pages 58–59.

Orange battery icon
If you see this page 57.

If the auto-injector turns off automatically, press and release the green button:
If the auto-injector is not responding with no icons lighting up page 56.
If any progress bar elements or icons light up page 61–63.

You see slowly flashing green mixing icon and the progress bar is frozen.

You hear a repeating notification sound.

Mixing paused (Step 4 on page 30 or Step 6 on page 36). If the SKYTROFA Auto-Injector is not in an upright position, mixing or air removal will pause (see Figure AD).

Do this: Place the auto-injector in an upright position and the mixing or air removal will continue.

Figure AD

You see a slowly flashing green check mark icon and the progress bar is frozen.

You hear a repeating notification sound.

Injection paused (Step 9 on page 42). If the green top is removed from the skin before completing the injection, the auto-injector will pause the injection (see Figure AE).

Do this: Press the green top against skin and the injection will start again. If the injection is not completed within 15 minutes, the auto-injector automatically cancels the injection.

Figure AE

You see a flashing green battery icon.

Charging recommended. There is enough battery for at least 1 injection.

Do this: Charge the auto-injector after the next injection.

You see a constant green battery icon.

Battery is fully charged. The auto-injector is ready to use (the battery icon turns off while the auto-injector is in use).

Do this: If you are charging the auto-injector, disconnect it from the charger.

You see no icons lighting up at all.

Either the auto-injector has turned off (the auto-injector will turn off if it is not active for 6 minutes without a cartridge loaded or for 3 minutes with a cartridge loaded) or the battery needs charging.

Do this: Press the green button to turn it on again.

1. If you see a flashing orange battery icon, the battery needs charging. Read more page 57.
2. If you see any other icons or the progress bar light up, the auto-injector has timed out and turned off automatically. Read more page 60.

You see a flashing orange battery icon. You hear a notification sound.

The battery needs charging.

Do this: Charge the auto-injector.

Insert the charging cable into the auto-injector at rear lower side and connect to a power outlet (see Figure AF). When the auto-injector has charged for 15 minutes and the battery icon flashes green, the auto-injector is ready to use for at least 1 injection after the charging cable is unplugged. When the battery icon shows constant green, the auto-injector is fully charged and lasts for at least 3 injections.

Figure AF

You see a flashing orange mixing icon.

You hear an error sound.

Either you have inserted a used cartridge, or you have canceled the mixing, or the auto-injector has canceled the injection, or the cartridge is damaged. The auto-injector cancels the injection 2 hours after automatic mixing (Step 4, page 30) or 2 hours after manual mixing (Step 5, page 32) is completed.

Do this: Remove the cartridge and wait for the device to turn off. Start again with a new, unused cartridge and make sure to screw on the needle straight and tightly.
Read more page 20.

You see a flashing orange check mark icon.

You hear an error sound.

Either an injection error has happened (the needle is not screwed on tightly, or it is bent or blocked), or you have canceled the injection, or the auto-injector has canceled an injection that was not completed within 15 minutes.

Do this: Remove the cartridge and wait for the auto-injector to turn off. Start again with a new, unused cartridge and make sure to screw on the needle straight and tightly.
Read more page 20.

You see 3 flashing icons alternating between green and orange.

You hear a repeating error sound.

The auto-injector is near its expiration. The first time you see this, either there are 5 injections left or the auto-injector expires in 1 month.

Do this: Press and release the green button to proceed. The green top will start flashing. The auto-injector can be used as usual for the remaining injections. When there are no more injections left or the expiration date has passed, the auto-injector cannot be used. Please contact a healthcare provider or Ascendis Pharma Customer Support to receive a new auto-injector. For Ascendis Pharma contact information back cover.

You see 3 flashing orange icons.

You hear an error sound.

Either the auto-injector has expired (the maximum number of injections has been reached or the lifetime of 5 years has passed) or a critical error has occurred.

Do this: Try to turn the auto-injector on (press and release the green button). If you still see 3 flashing orange icons, the auto-injector needs to be replaced. For disposal information page 73. Please contact a healthcare provider or Ascendis Pharma Customer Support to receive a new auto-injector. For Ascendis Pharma contact information back cover.

If you see no icons lighting up at all.
Either the auto-injector needs charging or it has timed out and turned off automatically.

Do this: Press and release the green button to turn the auto-injector on again.

1. If you see an orange flashing icon when you press the green button, the battery needs charging.

Do this: Read more page 57.

2. The auto-injector might have timed out and turned off automatically. If so, it will light up in one of the five different ways you see on the next pages.

Do this: Read the next pages and find the way your device lights up and blinks.

Situation A
You see a flashing green mixing icon and a progress bar with the bottom first element lit up. You hear a repeating notification sound.
The auto-injector has not completed the automatic medicine mixing.
Do this: Keep the auto-injector standing upright on a flat surface. Go to Step 4.1 on page 30.

Situation B
You see a constant green mixing icon and a flashing progress bar.
The auto-injector has not completed the manual mixing of the medicine.
Do this: Continue to turn the auto-injector up and down to mix the medicine by hand. Go to Step 5.1 on page 32.

Situation C
You see a flashing green mixing icon and a constant progress bar lit up. You hear a repeating notification sound.
The auto-injector has not automatically removed the air.
Do this: Keep the auto-injector standing upright on a flat surface. Go to Step 6.1 on page 36.

Situation D
You see a constant green mixing icon and a constant progress bar lit up.
You have not pulled off the needle cover within 3 minutes of completing automatic air removal.
Do this: Continue to pull off the needle cover. Go to Step 6.2 on page 37.

Situation E
You see a constant green eye icon.
You have not started to inject within 3 minutes of pulling off the needle cover.
Do this: Continue to prepare and do the injection. Go to Step 7 to Step 9, pages 38–43.

Cleaning and Maintenance

Cleaning the SKYTROFA Auto-Injector
If the auto-injector is dirty or if medicine has been spilled onto it, clean with a damp cloth. Before cleaning, the cartridge must be removed.
The green top needs to be cleaned on the outside and on the reachable part of the inside.
If medicine is spilled inside the auto-injector, turn it upside down to let the medicine run out.

Do not clean the auto-injector while charging. Keep the auto-injector dry.
Do not place the auto-injector in liquid.
Do not sterilize the auto-injector.

Maintenance of the SKYTROFA Auto-Injector

Do not open, try to repair, or change the auto-injector. The battery is not replaceable. Please call Ascendis Pharma Customer Support. For contact information back cover.

Charging and Charging Cable

Charging the SKYTROFA Auto-Injector

Connect the USB (large end of the cable) to the charger. Plug the charger into a power outlet. Connect the Micro-USB (small end of the cable) to the rear of the auto-injector. For protection, charge the auto-injector with the protective cover on. Read more pages 12–13.
Only charge the auto-injector when the battery icon is flashing green or orange. Read more pages 56–57.

Do not use any charger or charging cables other than those included with your auto-injector. Other chargers or cables may create problems and may interfere with device operation.

Do not clean the auto-injector while charging. Keep the auto-injector dry.

Do not insert a cartridge when the auto-injector is connected to the charger.

Do not attempt to insert the charging cable in the auto-injector if a cartridge has been inserted.

Storing

Storing the SKYTROFA Auto-Injector

Keep out of the reach of children.
This product contains small parts that may present a choking hazard to small children. The cable can present a strangulation hazard.

Do not store the auto-injector closer than 12 inches (30 cm) to microwave ovens or electronic equipment with antennas such as Wi-Fi transceivers. The auto-injector may not work the right way.
Remove the cartridge from the auto-injector before storing.
Store with the protective cover on.
It is recommended to store the auto-injector at room temperature between 59°F to 86°F (15°C to 30°C), in between uses. If the auto-injector is stored at higher or lower temperatures, you should keep it at room temperature for 30 minutes before use with a cartridge. The auto-injector can be stored between 14°F to 104°F (-10°C to 40°C) if not in use.
Keep the protective cover on when traveling with the auto-injector.
Keep the auto-injector away from dirt, dust, and humid or wet places.
Keep the auto-injector, the charger, and the charging cable away from pets and pests.
Avoid refrigerating or freezing the auto-injector in between uses.

Avoid exposing the auto-injector to direct sunlight and extreme temperatures.
For technical details of the conditions under which the auto-injector can be used, stored, and transported pages 77-79.
Storing the SKYTROFA Cartridge
For information on the SKYTROFA Cartridge storing, see instructions on the cartridge pack and blister.

Product Information

 | Page
Product Safety | 70
Expiration | 72
EMC Compliance Levels | 74
Technical Specification | 77
Symbols | 80
Warranty and Disclaimer | 84
Parts Overview | 85

Product Safety

Do not use the SKYTROFA Auto-Injector if the SKYTROFA Cartridge cannot be inserted or removed, or if the cartridge was not completely emptied during the last attempted injection.

Do not use the auto-injector if you think it may be damaged.

Do not open, try to repair, or change the auto-injector. The battery is not replaceable. Please call Ascendis Pharma Customer Support. For contact information back cover.

Do not clean the auto-injector while charging. Keep the auto-injector dry.

Do not use or place the auto-injector closer than 12 inches (30 cm) to microwave ovens or electronic equipment with antennas such as Wi-Fi transceivers. The auto-injector might not work the right way.

Do not use a cartridge if it has been dropped or you think it may be damaged.

Do not expose the auto-injector to extreme temperatures. Keep the auto-injector away from heat and open flames. Keep it out of direct sunlight.
Do not place the auto-injector in liquid.
Do not wash the auto-injector in a dishwasher.

Expiration

The SKYTROFA Auto-Injector has an expiration date (5 years after the manufacturing date) or a maximum of 210 injections, whichever comes first. The expiration date is located at the bottom of the auto-injector and is indicated by year (YYYY), month (MM), and date (DD), printed as YYYY-MM-DD.
When there are 5 injections or less than 1 month left, the auto-injector will indicate this when turned on. Read more page 59.
The auto-injector may be used for the remaining 5 injections. After the final injection or after the expiration date, your auto-injector has to be replaced. Please contact a healthcare provider or Ascendis Pharma Customer Support to receive a new auto-injector. For contact information back cover.
The auto-injector contains electrical and electronic components, including a non-replaceable battery.
Do not throw away (dispose) in household trash.
When the auto-injector reaches its expiration date, maximum number of injections, or needs replacing, return it to the Ascendis Pharma Customer Support. Contact Ascendis Pharma Customer Support for instructions on how to return properly. For contact information back cover.

EMC Compliance Levels

The auto-injector is intended for use in the electromagnetic environment specified below. The user of the auto-injector should ensure that it is used in such an environment.

Electromagnetic Compatibility (EMC) Compliance Levels | Basic EMC Standard
EMC - RF Field radiated emission in 10 m (maximum): a) 30 MHz to 230 MHz: ≤ 30 dB (μV/m) quasi-peak. b) 230 MHz to 1 GHz: ≤ 37 dB (μV/m) quasi-peak. c) Internal source <108 MHz Compliance levels according to CISPR11, Group1, Class B. | IEC 60601-1-2 Edition 4.1/ EN 60601-1-2:2015/ A1:2021 CISPR 11 / EN 55011 EN ISO 11608- 4:2022
EMC - RF Field radiated immunity - Electrical field: a) 10 V/m 80-2700 MHz. 1 kHz 80% AM | IEC 60601-1-2 Edition 4.1/ EN 60601-1-2:2015/ A1:2021 IEC 61000-4-3 EN ISO 11608- 4:2022
EMC - Power Frequency Magnetic field, Immunity: a) 30 A/m | IEC 60601-1-2 Edition 4.1/ EN 60601-1-2:2015/ A1:2021 IEC 61000-4-3 EN ISO 11608- 4:2022
EMC - Fast transients and bursts: a) Fast transients and bursts ±2 kV ac mains | IEC 60601-1-2 Edition 4.1/ EN 60601-1-2:2015/ A1:2021 IEC 61000-4-4 EN ISO 11608-4:2022
EMC - Surge: a) Surge ±1 kV Line-to-Line ac mains | EC 60601-1-2 Edition 4.1/ EN 60601-1-2:2015/ A1:2021 IEC 61000-4-5 EN ISO 11608-4:2022
EMC - Conducted immunity disturbance by RF fields a) 3 Vrms 150 kHz to 80 MHz (6 Vrms in ISM and amateur radio bands) | IEC 60601-1-2 Edition 4.1/ EN 60601-1-2:2015/ A1:2021 IEC 61000-4-6 EN ISO 11608-4:2022
EMC - Conducted emission a) 150 kHz-30 MHz 120 V @ 60 Hz Compliance levels according to CISPR11, Group1, Class B. | IEC 60601-1-2 Edition 4.1 EN 60601-1-2:2015/ A1:2021 CISPR 11/EN 55011 EN ISO 11608-4:2022
EMC - Voltage dips and interruptions: a) <5% UT for 5 sec b) <5% UT for 0.5 cycles c) 70% UT for 25 cycles d) 40% UT for 5 cycles | IEC 60601-1-2 Edition 4.1/ EN 60601-1-2:2015/ A1:2021 IEC 61000-4-11 EN ISO 11608-4:2022
EMC - RF Field Immunity to Proximity fields from Wireless communication equipment, Immunity at 0.3 m separation: a) 27 V/m @ 380-390 MHz b) 28 V/m @ 430-470 MHz c) 9 V/m @ 704-787 MHz d) 28 V/m @ 800-960 MHz e) 28 V/m @ 1700-1990 MHz f) 28 V/m @ 2400-2570 MHz g) 9 V/m @ 5100-5800 MHz | IEC 60601-1-2 Edition 4.1/EN 60601-1-2:2015/ A1:2021 IEC 61000-4-39 EN ISO 11608- 4:2022
EMC - Immunity to proximity magnetic fields (9 kHz to 13.56 MHz): a) 30 kHz - CW modulation - 8 A/m b) 134.2 kHz - 2.1 kHz pulse modulation - 65 A/m c) 13.56 MHz - 50 kHz pulse modulation - 7.5 A/m | IEC 60601-1-2 Edition 4.1/EN 60601-1-2:2015/ A1:2021 IEC 61000-4-39 EN ISO 11608- 4:2022
ESD immunity: a) ± 8 kV contact b) ± 2, 4, 8 and 15 kV air | IEC 60601-1-2 Edition 4.1/EN 60601-1-2:2015/ A1:2021 IEC 61000-4-2 EN ISO 11608- 4:2022

Technical Specification

SKYTROFA Auto-Injector
Lifetime | Expiration date page 72.
Serial Number (SN) | Please refer to the bottom side of your auto-injector, marked after.
Size | 7.09 × 1.46 × 1.06 in (180 × 37 × 27 mm).
Weight | 5.29 oz (150 g).
Display | Light-emitting diodes (LED).
Power source | Mains charger: 100 to 240 V AC.
Power supply | 1 rechargeable internal Li-ion battery.
Full capacity charging time | 2 hours and 30 minutes. Charging time for 1 injection: 15 minutes.
Full capacity | 3 weeks with 1 injection per week.
Electromagnetic compatibility | SKYTROFA Auto-Injector meets the requirements of IEC / EN 60601-1- 2, 4-th Edition. Using SKYTROFA Auto-Injector in the immediate vicinity of microwave appliances may result in impaired functioning. Use and store SKYTROFA Auto-Injector outside such an environment.
Protection against electric shock | Type BF.
Dose accuracy | SKYTROFA Auto-Injector meets the requirements of ISO 11608-1:2022. Minimum 90% of the volume.
Needle Insertion Depth | Based on needle length of 4 mm.
Ingress protection | IP22: IP2X: Ingress protection of solid foreign objects, ≥ 12.5mm diameter. IPX2: Ingress protection of water with harmful effects, dripping (15% tilted). Both put together called IP22.
Cable | USB to Micro-USB cable, 1m.
Bluetooth® Version | BLE v5.3 with frequency 2.4 GHz.
Software Bill of Materials | The off-the-shelf software components that are used in the SKYTROFA Auto-Injector can be found on: https://www.phillipsmedisize. com/sbom

Charger
Model | ASSA54a-050100.
Input | 100-240V – 50-60Hz.
Output | 5.0V 1.0A.

Use Conditions for SKYTROFA Auto-Injector
Operation temperature (with medicine) and recommended storage temperature in between uses | 59°F to 86°F (15°C to 30°C) (marking on device bottom).
Storage & Transportation temperature | 14°F to 104°F (-10°C to 40°C) (marking on device cover).
Charging temperature | 59°F to 86°F (15°C to 30°C).
Operation humidity | 15 to 90% relative humidity, non-condensing.
Storage & Transportation relative humidity | Up to 93% relative humidity, non-condensing.
Atmospheric pressure | 10.15 psi to 15.37 psi (700 hPa to 1060 hPa).

Use Conditions for Cartridge with Medicine and Needles

The use conditions provided here are for the SKYTROFA Auto-Injector device. The use conditions for SKYTROFA Cartridges with medicine and needles may be different. To see the use conditions for cartridges with medicine and needles, please see the information provided with your medicine.

Waste

To protect natural resources and to promote material reuse, please separate packaging material from electronic, medicine, and sharp waste and recycle the material through your local recycling system.

Electronic waste: The auto-injector, including battery, must be returned to the manufacturer. Contact Ascendis Pharma Customer Support for instructions on how to return properly back cover.

Charger and USB cable must be disposed of following local regulations for disposal of electronic waste.

Symbols

These symbols are found on the SKYTROFA Auto-Injector, the packaging, and the Instructions for Use.

Manufacturer.

Distributor.

Unique serial number of SKYTROFA Auto-Injector.

Model Number.

Manufacturer catalogue number for identification.

Manufacturer batch code for identification.

Medical Device.

Single patient Multiple use.

Expiration date.

Consult Instructions For Use.

Applied parts
SKYTROFA Auto-Injector is a type BF device and provides protection against electrical shock and electrical current leakage. Applied parts on the device are the green top, the housing, and the button.

Warning!
When this warning symbol is seen, safety instructions must be followed. Otherwise, serious safety hazardous situations and injuries may occur.

Precaution!
When this precaution symbol is seen, safety instructions must be followed. Otherwise, minor to moderate safety hazardous situations and injuries and potential damage to the auto-injector or other property may occur.

Rx only

Caution: Federal law restricts this device for sale by or on the order of a physician.

Operation temperature.

Storage & Transportation temperature.

Keep dry.

If the auto-injector packaging has been damaged or unintentionally opened before the first use, contact customer support back cover.

SKYTROFA Auto-Injector contains electrical and electronic components, including a battery that cannot be replaced, and must not be disposed of using standard waste collection.

SKYTROFA Auto-injector packaging is a non-corrugated fiberboard. Can be disposed of as paper.

SKYTROFA Auto-Injector has been tested and found to comply with the limits for a Class B digital device, according to part 15 of the FCC Rules.

Radio transmitter – Bluetooth® technology @2.4GHz using customized encrypted protocol – ClassB digital device.

DC (Direct Current).

Bluetooth® technology

Pairing key.

The Unique Device Identifier (UDI) that appears on the carton is shown by a barcode and human readable format:
(01) Device Identifier
(10) Batch Number
(17) Expiry date in YYMMDD format
(21) Serial Number

FCC Class B Notice

It is not allowed to modify the SKYTROFA Auto- Injector. Modifications may void the authority granted to the user by the FCC to operate this equipment.

This device complies with Part 15 of the FCC Rules. Operation is subject to the following two conditions:

1. This device may not cause harmful interference.
2. This device must accept any interference received, including interference that may cause undesired operation.

Note: This equipment has been tested and found to comply with the limits for a Class B digital device, pursuant to Part 15 of the FCC Rules.

These limits are designed to provide reasonable protection against harmful interference in a residential installation. This equipment generates, uses and can radiate radio frequency energy and, if not installed and used in accordance with the instructions, may cause harmful interference to radio communications. However, there is no guarantee that interference will not occur in a particular installation. If this equipment does cause harmful interference to radio or television reception, which can be determined by turning the equipment off and on, the user is encouraged to try to correct the interference by one or more of the following measures:

- Reorient or relocate the receiving antenna.
- Increase the separation between the equipment and receiver.
- Connect the equipment into an outlet on a circuit different from that to which the receiver is connected.
- Consult the dealer or an experienced radio/television technician for help.

Warranty and Disclaimer

Warranty

After the expiration date, your SKYTROFA Auto-Injector must be replaced. Please contact a healthcare provider or Ascendis Pharma Customer Support to receive a new auto-injector. For contact information back cover.

The expiration date is located at the bottom of the auto-injector and is indicated by year (YYYY), month (MM), and date (DD), printed as YYYY-MM-DD.

Disclaimer

The correct application of SKYTROFA according to the information provided with your medicine remains your responsibility.

Ascendis Pharma Endocrinology Inc. shall have no liability for incidental or consequential damages.

We reserve the right to modify technical specifications and documentation.

Patent Information

www.ascendispharma.us/products/patents

Parts Overview

Quick Reference Guide

Skytrofa® Auto-Injector
For SKYTROFA cartridges

Single-patient use

This is your
Quick Reference Guide

- Read your Instructions for Use for full instructions before using this Quick Reference Guide.
- For training video, go to www.skytrofa.com
- If you are unsure about your dose, contact your healthcare provider.

Instructions for Use

Quick Reference Guide

Training Video

Ascendis Pharma Customer Support

1-844-44ASCENDIS
(1-844-442-7236)

# | 02 2025-07-18 8020100531_05

Parts overview

Constant green
Battery is fully charged
The SKYTROFA
Auto-Injector is ready to use

Flashing green
At least 1 injection remaining, but charging recommended after use

Flashing orange
Battery needs charging

Quick troubleshooting

For all troubleshooting cases and details, see Instructions for Use (IFU)

IFU page 52

Charging required (Step 2)

IFU page 57

If the battery level is low:

You will see a flashing orange battery icon.

Do this: Insert charging cable into the SKYTROFA Auto-Injector at rear lower side and connect to a power outlet.

SKYTROFA Auto-Injector not upright (Step 4 and 6.1)

IFU page 54

If the SKYTROFA Auto-Injector is not in an upright position during mixing and air removal:

You will hear a repeating notification sound. Mixing icon will flash slowly and progress bar will freeze.

Do this: Place the SKYTROFA Auto-Injector in an upright position and the mixing or air removal will continue.

Skin contact lost (Step 9)

IFU page 55

If the green top is removed from skin before the injection is complete:

You will hear a repeating notification sound. Check mark icon will flash slowly and progress bar will freeze.

Do this: Press green top against skin and the injection will continue.

Prepare

1 Check and assemble cartridge and needle

1.1 | 1.2 |  | 1.3
Check expiration date and cartridge dose on cartridge pack. If refrigerated, allow 15 minutes to reach room temperature. |  |  | Screw needle straight and tightly on cartridge. Do not remove needle cover.
Check expiration date and cartridge dose on cartridge pack. If refrigerated, allow 15 minutes to reach room temperature. | Remove paper from needle. |  | Screw needle straight and tightly on cartridge. Do not remove needle cover.

2 Turn on the auto-injector

(You will hear 2 loud beeps. Battery icon will light up and green top will start flashing)

3 Insert cartridge with attached needle

 | 3.1 |  | 3.2 |  | 3.3

Mix

4 Wait while mixing

Wait 4 to 8 minutes for the auto-injector to mix medicine. Watch progress bar gradually light up. |  | Wait until you hear 2 loud beeps and the entire progress bar flashes.

If your auto-injector turns off automatically read Instructions for Use
IFU page 60.

5 Turn the auto-injector up and down

Turn the auto-injector up and down, listening for a tick sound each up and down cycle to make sure the turns are correct. Turn up and down correctly 5 to 10 times until you hear 2 loud beeps and the whole progress bar, except the top element, lights up. Do not press the green button.

If you see a flashing orange mixing icon read IFU page 58.

6 Finish mixing

 | 6.1 |  | 6.2
Keep the auto-injector upright on a flat surface until you hear 2 loud beeps and the entire progress bar lights up. |  |  | 6.2

Inject

7 Check mixed medicine

8 Prepare for injection

8.1 | 8.2 | 8.3
Choose an injection site: Stomach (abdomen), thighs, or buttocks. Change the injection site for every injection. | Make sure your hands are clean using soap and water or hand sanitizer. | Clean injection site with alcohol wipe. Do not inject through clothes.

9 Inject medicine

9.1 | 9.2

After injection

10 Remove cartridge

10.1 | 10.2

11 Check cartridge and throw away

12 Store the auto-injector

PRINCIPAL DISPLAY PANEL - 3 mg Cartridge Blister Pack Carton

Skytrofa®
(lonapegsomatropin-tcgd)
for injection

3 mg

Box with:
4 single-dose cartridges and
6 sterile injection needles

OPEN HERE

127883

NDC 73362-003-01

GTIN: 00373362003010

PRINCIPAL DISPLAY PANEL - 3.6 mg Cartridge Blister Pack Carton

Skytrofa®
(lonapegsomatropin-tcgd)
for injection

3.6 mg

Box with:
4 single-dose cartridges and
6 sterile injection needles

OPEN HERE

127889

NDC 73362-004-01

GTIN: 00373362004017

PRINCIPAL DISPLAY PANEL - 4.3 mg Cartridge Blister Pack Carton

Skytrofa®
(lonapegsomatropin-tcgd)
for injection

4.3 mg

Box with:
4 single-dose cartridges and
6 sterile injection needles

OPEN HERE

130972

NDC 73362-005-01

GTIN: 00373362005014

PRINCIPAL DISPLAY PANEL - 5.2 mg Cartridge Blister Pack Carton

Skytrofa®
(lonapegsomatropin-tcgd)
for injection

5.2 mg

Box with:
4 single-dose cartridges and
6 sterile injection needles

OPEN HERE

127882

NDC 73362-006-01

GTIN: 00373362006011

PRINCIPAL DISPLAY PANEL - 6.3 mg Cartridge Blister Pack Carton

Skytrofa®
(lonapegsomatropin-tcgd)
for injection

6.3 mg

Box with:
4 single-dose cartridges and
6 sterile injection needles

OPEN HERE

130973

NDC 73362-007-01

GTIN: 00373362007018

PRINCIPAL DISPLAY PANEL - 7.6 mg Cartridge Blister Pack Carton

Skytrofa®
(lonapegsomatropin-tcgd)
for injection

7.6 mg

Box with:
4 single-dose cartridges and
6 sterile injection needles

OPEN HERE

127886

NDC 73362-008-01

GTIN: 00373362008015

PRINCIPAL DISPLAY PANEL - 9.1 mg Cartridge Blister Pack Carton

Skytrofa®
(lonapegsomatropin-tcgd)
for injection

9.1 mg

Box with:
4 single-dose cartridges and
6 sterile injection needles

OPEN HERE

127885

NDC 73362-009-01

GTIN: 007373362009012

PRINCIPAL DISPLAY PANEL - 11 mg Cartridge Blister Pack Carton

Skytrofa®
(lonapegsomatropin-tcgd)
for injection

11 mg

Box with:
4 single-dose cartridges and
6 sterile injection needles

OPEN HERE

127884

NDC 73362-010-01

GTIN: 00373362010018

PRINCIPAL DISPLAY PANEL - 13.3 mg Cartridge Blister Pack Carton

Skytrofa®
(lonapegsomatropin-tcgd)
for injection

13.3 mg

Box with:
4 single-dose cartridges and
6 sterile injection needles

OPEN HERE

127881

NDC 73362-011-01

GTIN: 00373362011015

PRINCIPAL DISPLAY PANEL - 0.7 mg Cartridge Blister Pack Box

Skytrofa®
(lonapegsomatropin-tcgd)
for injection

0.7 mg

Box with:
4 single-dose cartridges and
6 sterile injection needles

OPEN HERE

127880

NDC 73362-012-01

GTIN: 00373362012012

LOT NNNNNNNN

Expiration YYYY-MM

SN NNNNNNNNNNNN

PRINCIPAL DISPLAY PANEL - 1.4 mg Cartridge Blister Pack Box

Skytrofa®
(lonapegsomatropin-tcgd)
for injection

1.4 mg

Box with:
4 single-dose cartridges and
6 sterile injection needles

OPEN HERE

127879

NDC 73362-013-01

GTIN: 00373362013019

LOT NNNNNNNN

Expiration YYYY-MM

SN NNNNNNNNNNNN

PRINCIPAL DISPLAY PANEL - 1.8 mg Cartridge Blister Pack Box

Skytrofa®
(lonapegsomatropin-tcgd)
for injection

1.8 mg

Box with:
4 single-dose cartridges and
6 sterile injection needles

OPEN HERE

127878

NDC 73362-014-01

GTIN: 00373362014016

LOT NNNNNNNN

Expiration YYYY-MM

SN NNNNNNNNNNNN

PRINCIPAL DISPLAY PANEL - 2.1 mg Cartridge Blister Pack Box

Skytrofa®
(lonapegsomatropin-tcgd)
for injection

2.1 mg

Box with:
4 single-dose cartridges and
6 sterile injection needles

OPEN HERE

127877

NDC 73362-015-01

GTIN: 00373362015013

LOT NNNNNNNN

Expiration YYYY-MM

SN NNNNNNNNNNNN

PRINCIPAL DISPLAY PANEL - 2.5 mg Cartridge Blister Pack Box

Skytrofa®
(lonapegsomatropin-tcgd)
for injection

2.5 mg

Box with:
4 single-dose cartridges and
6 sterile injection needles

OPEN HERE

127876

NDC 73362-016-01

GTIN: 00373362016010

LOT NNNNNNNN

Expiration YYYY-MM

SN NNNNNNNNNNNN